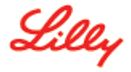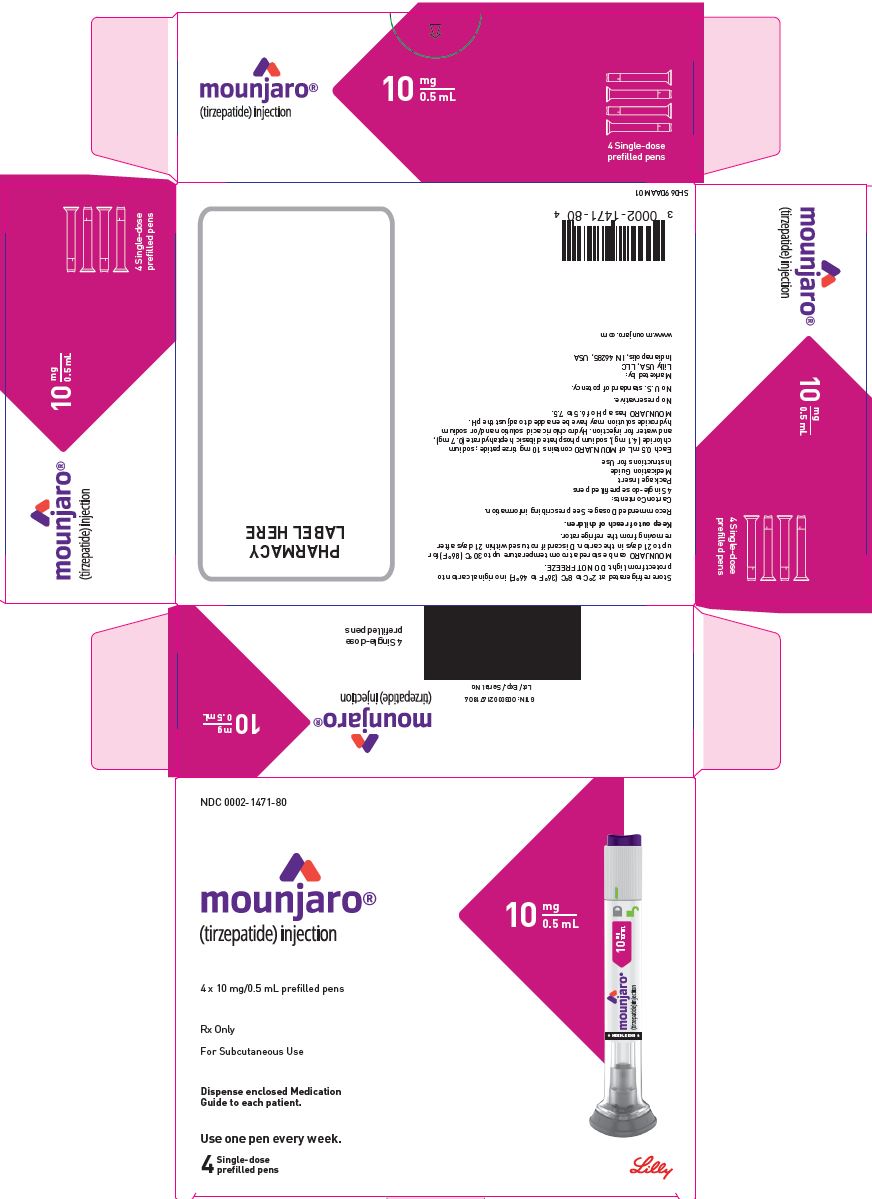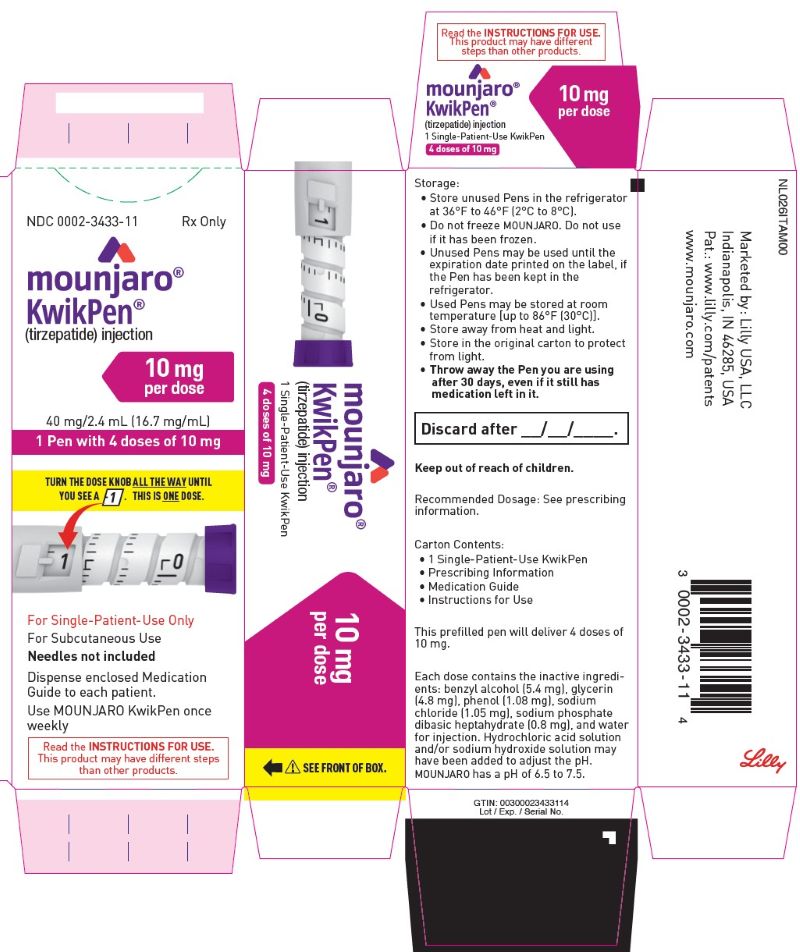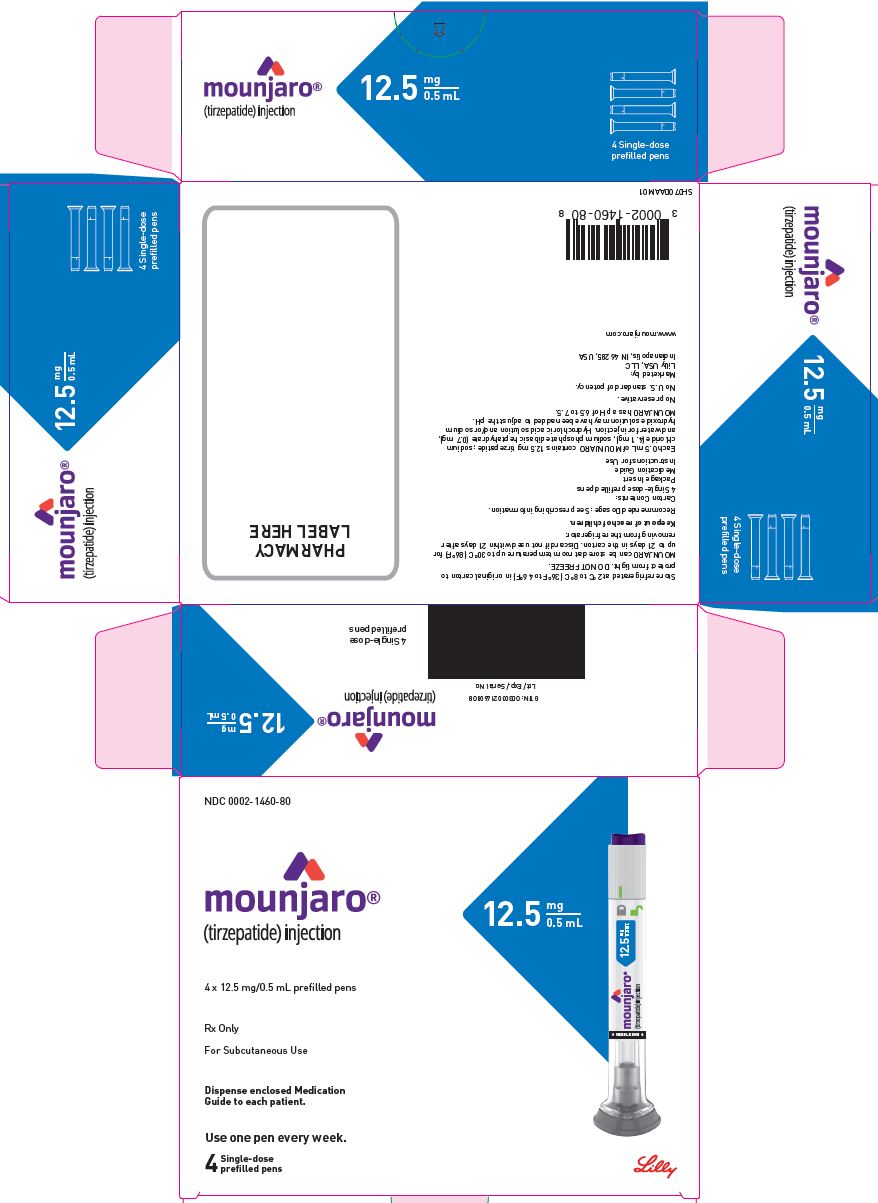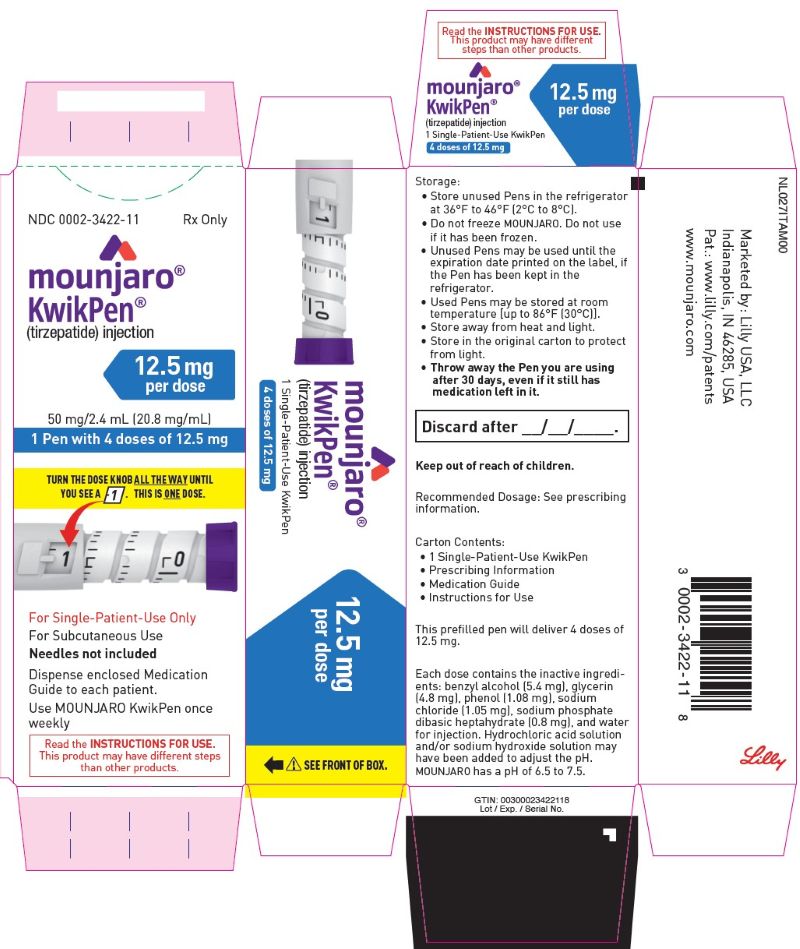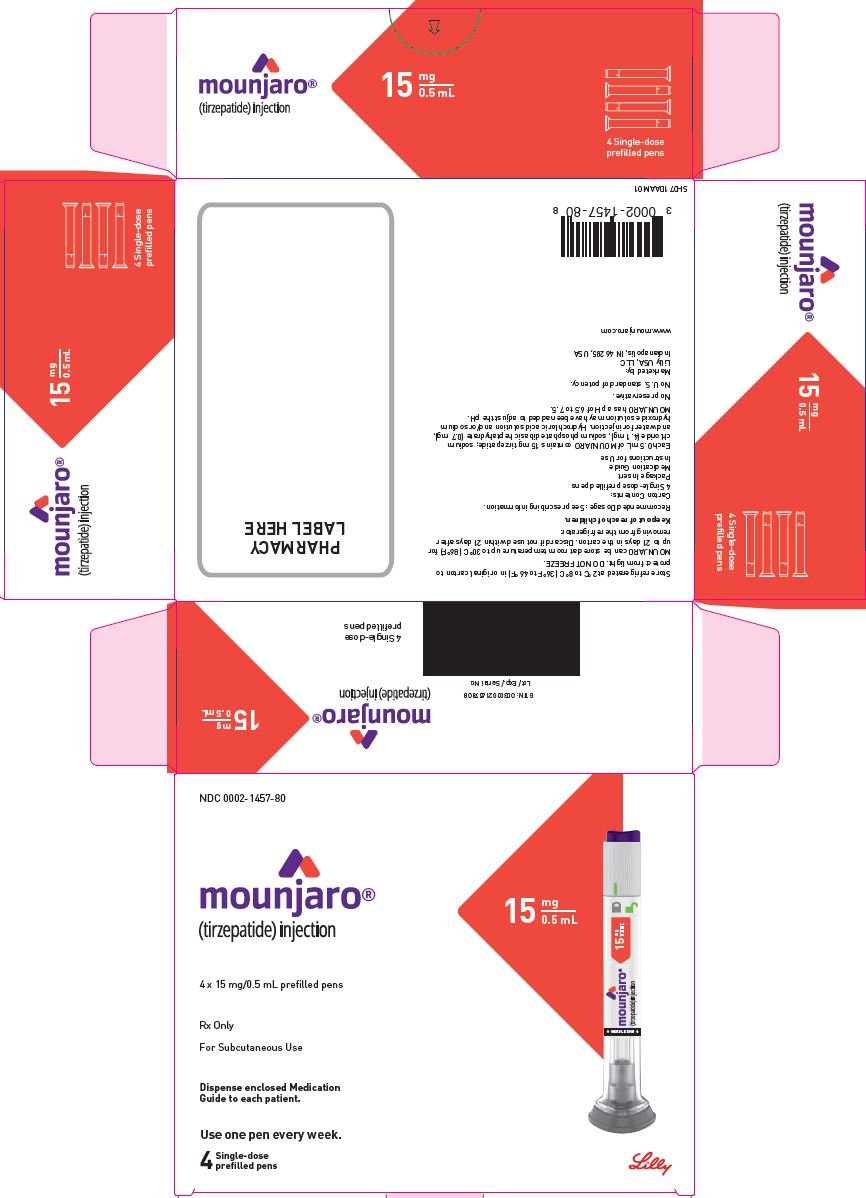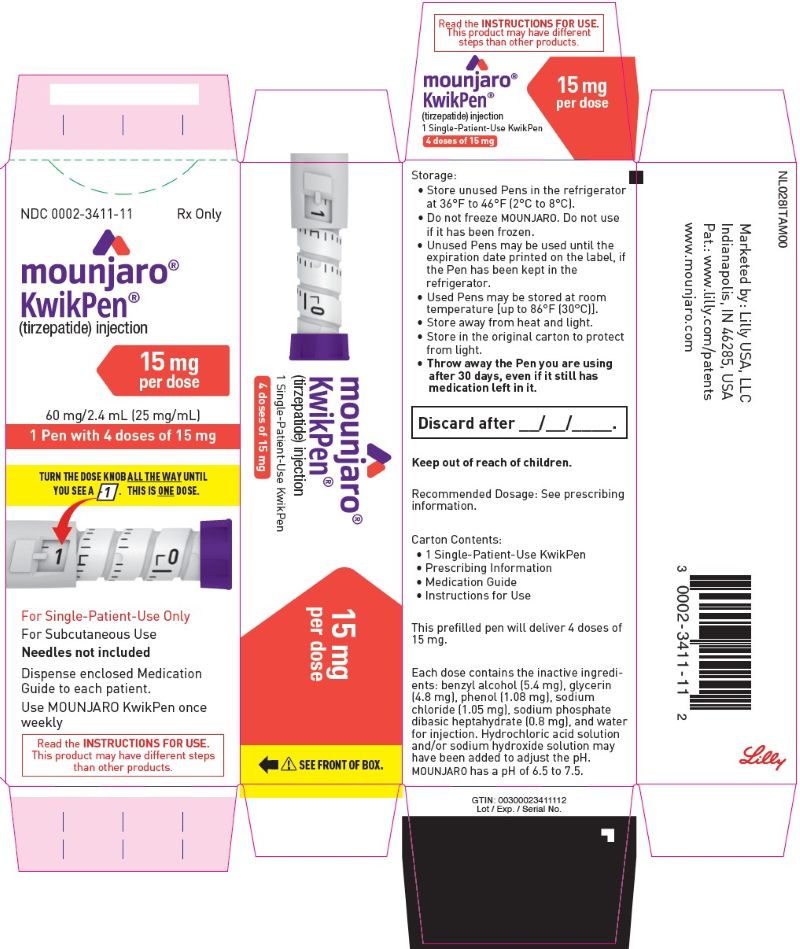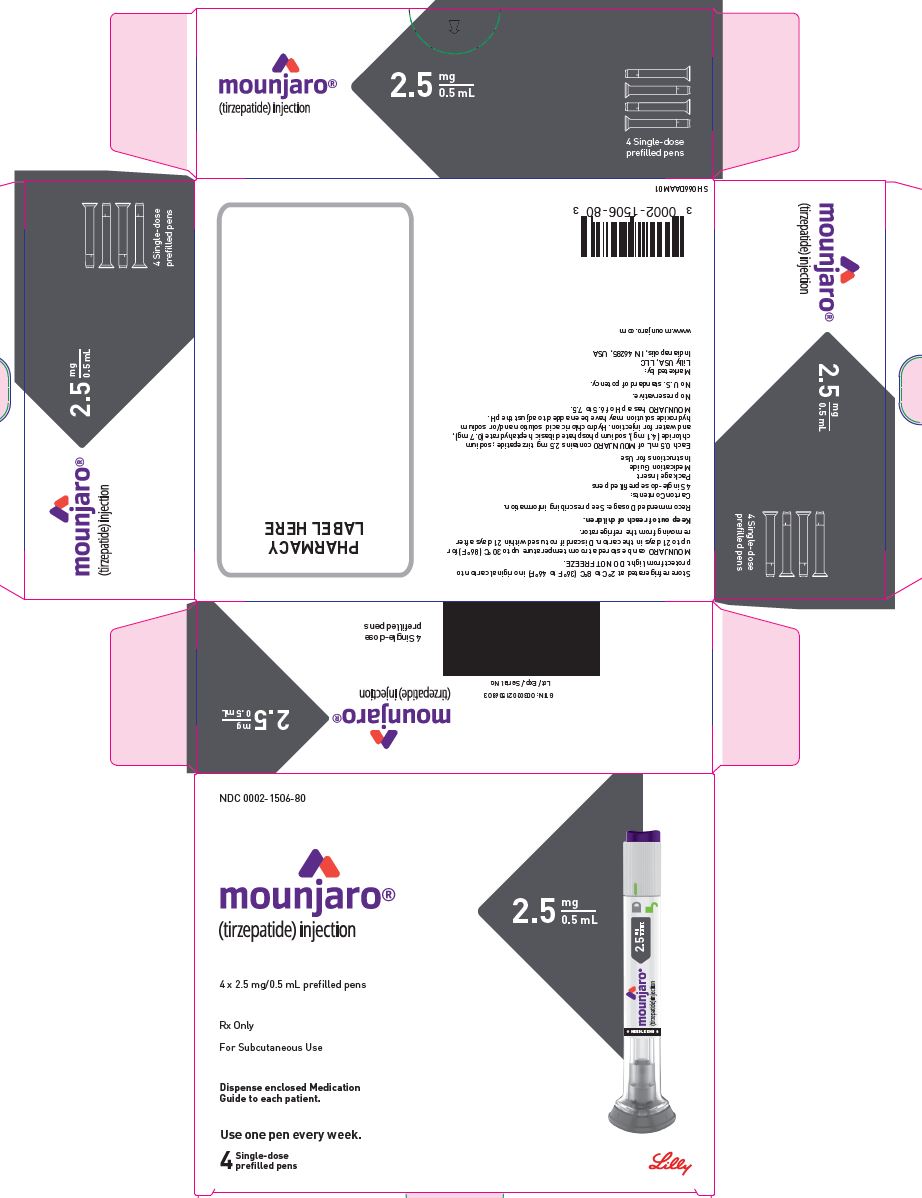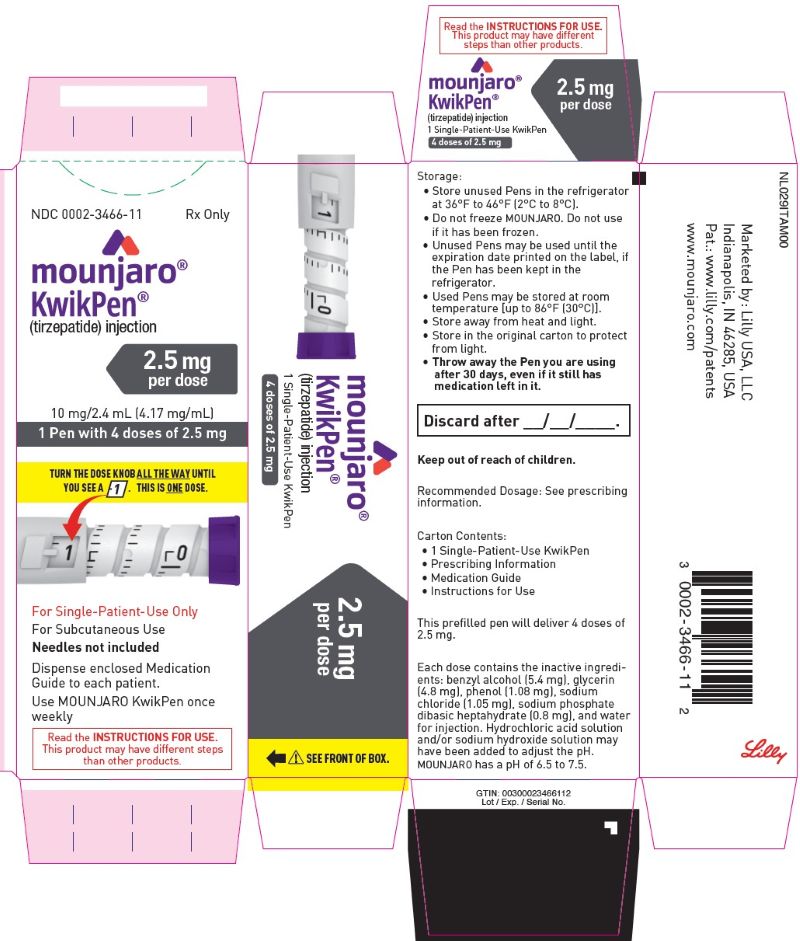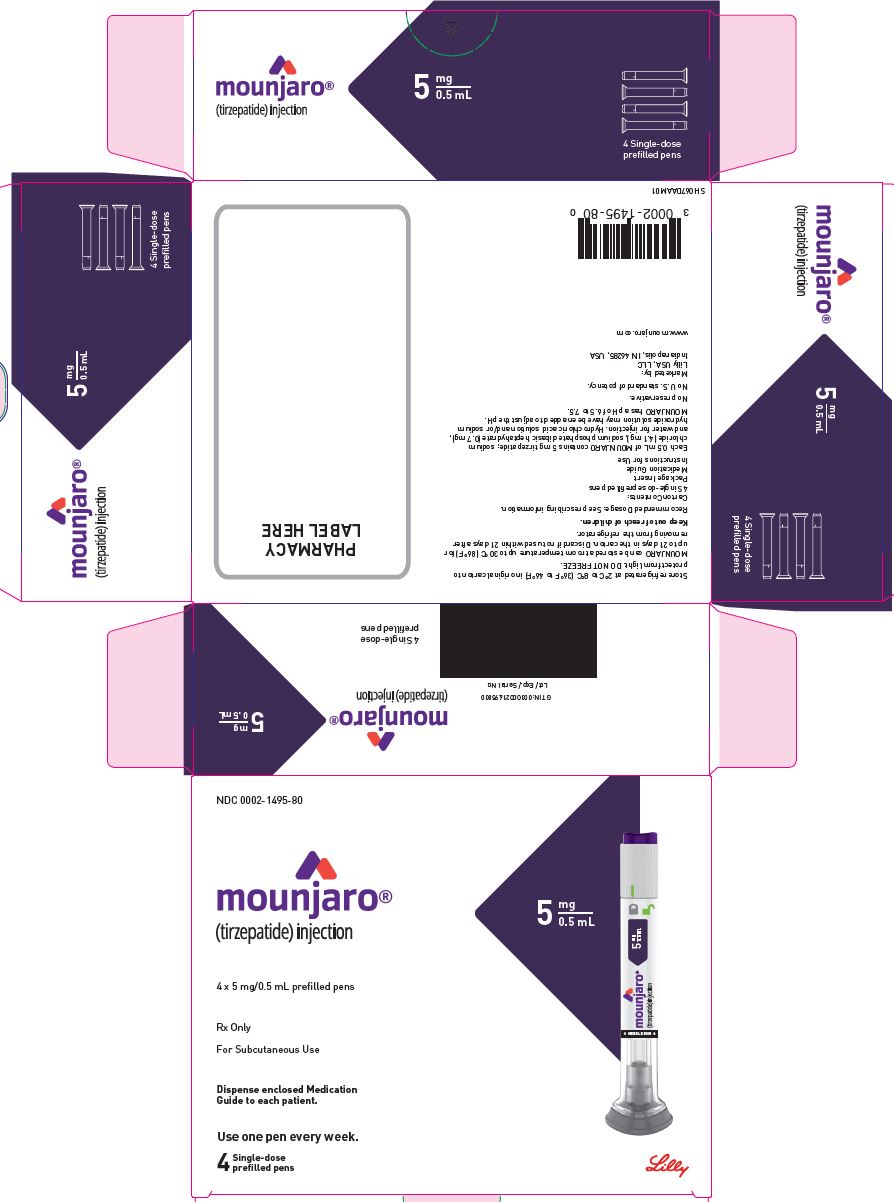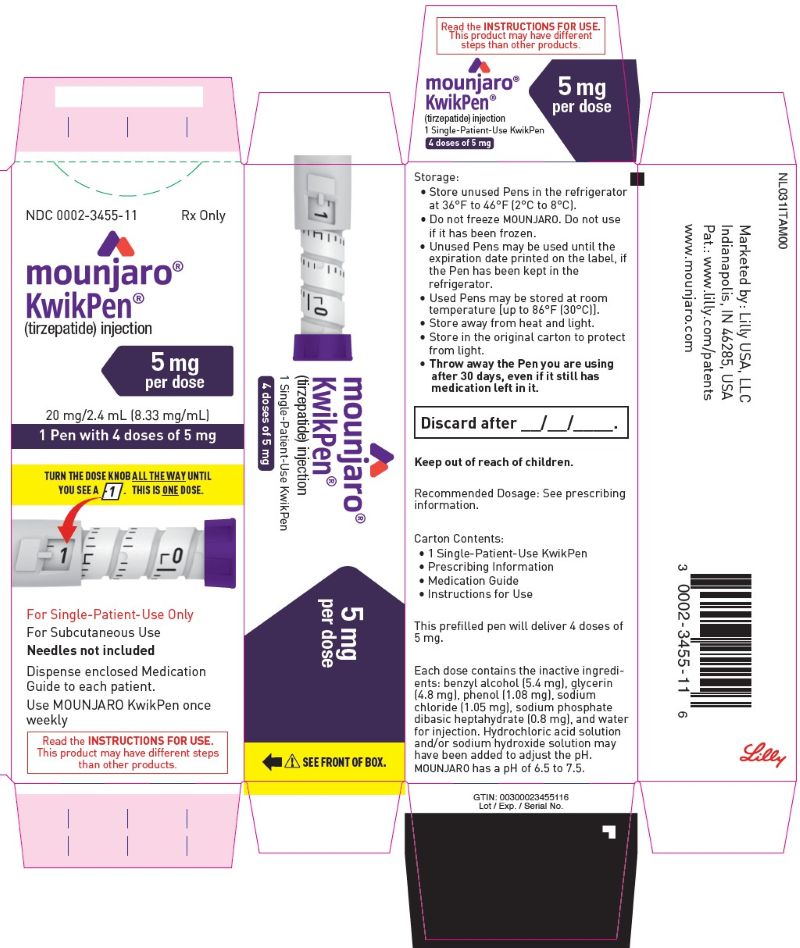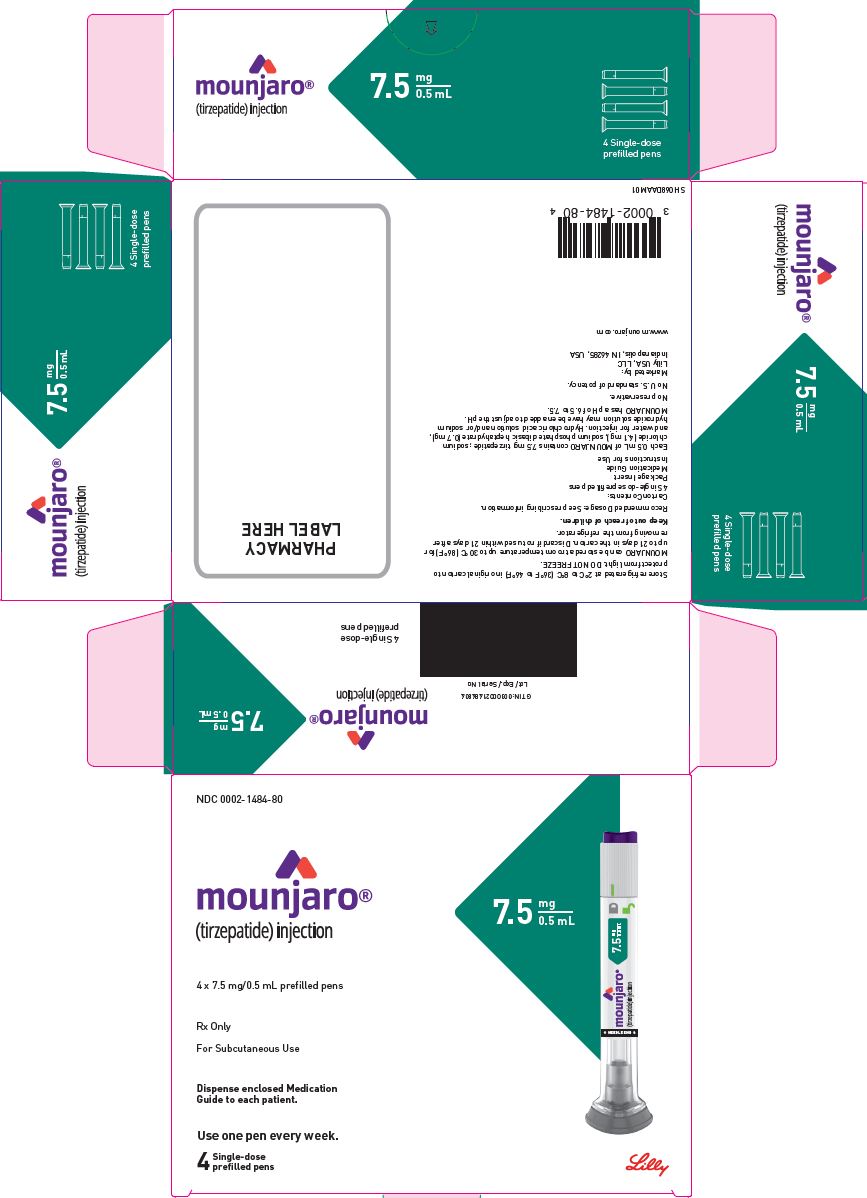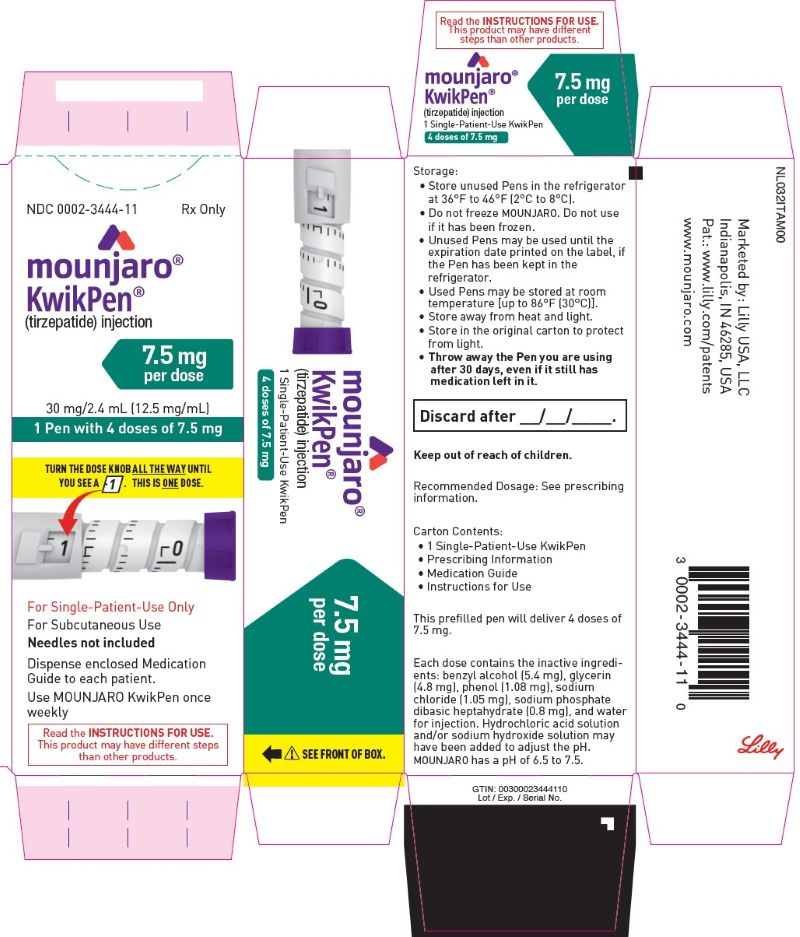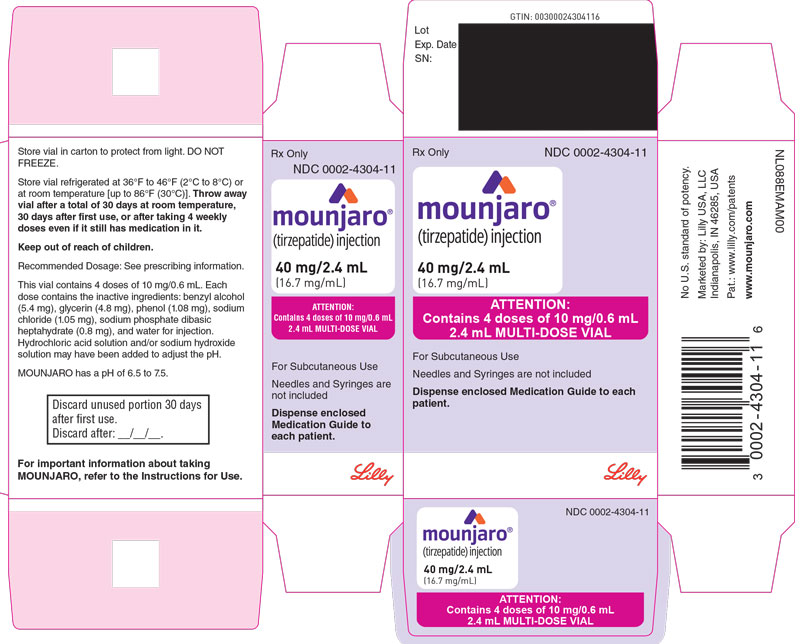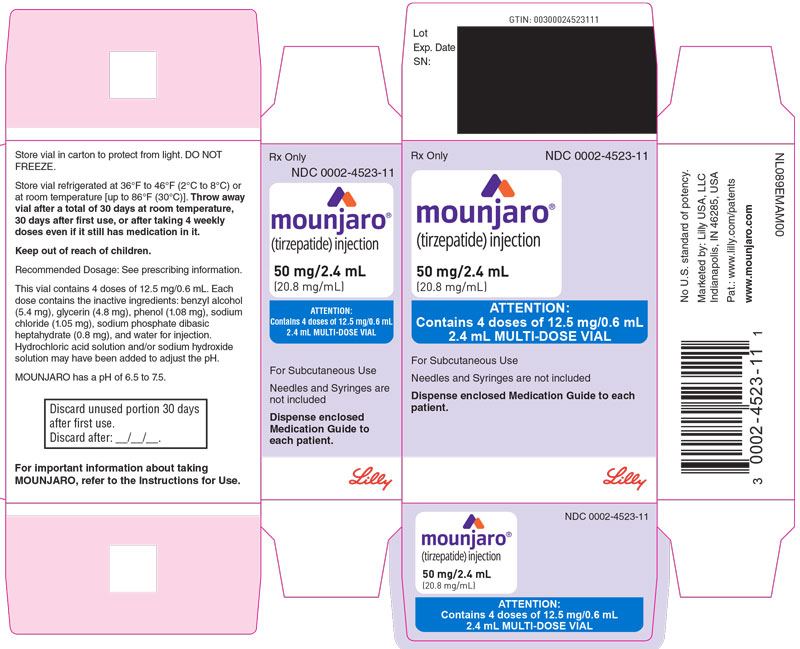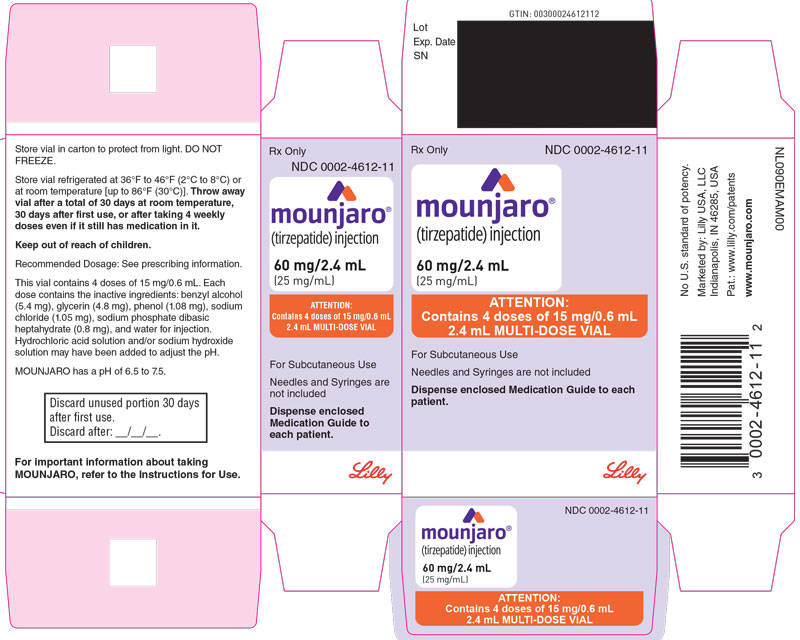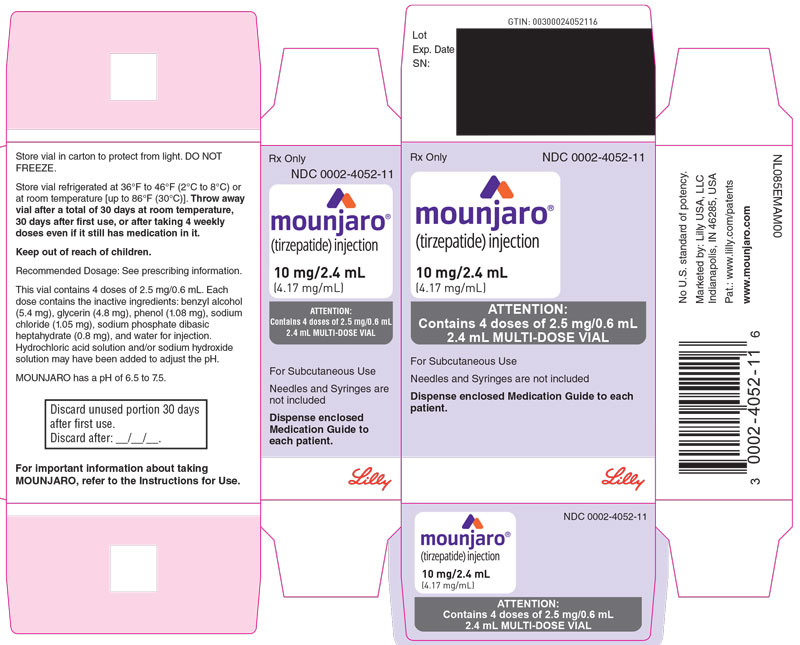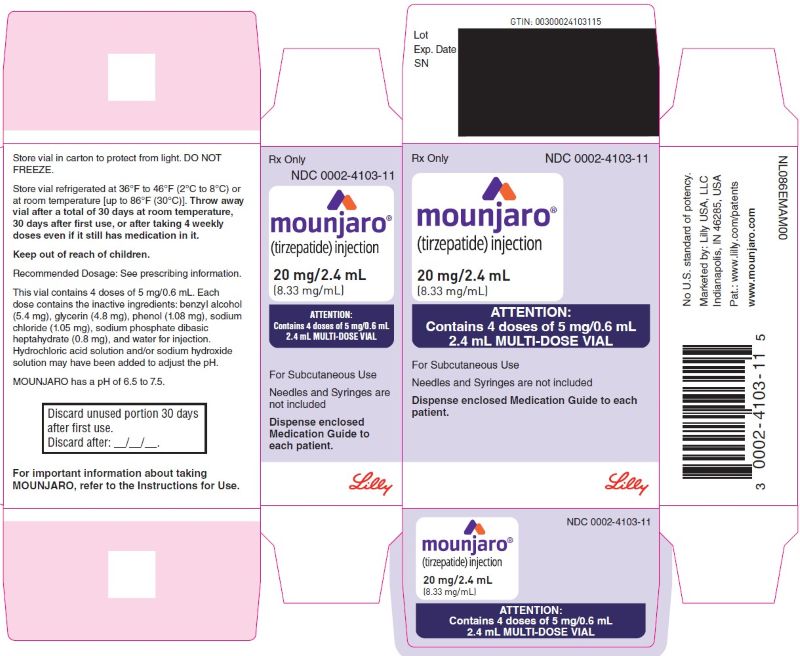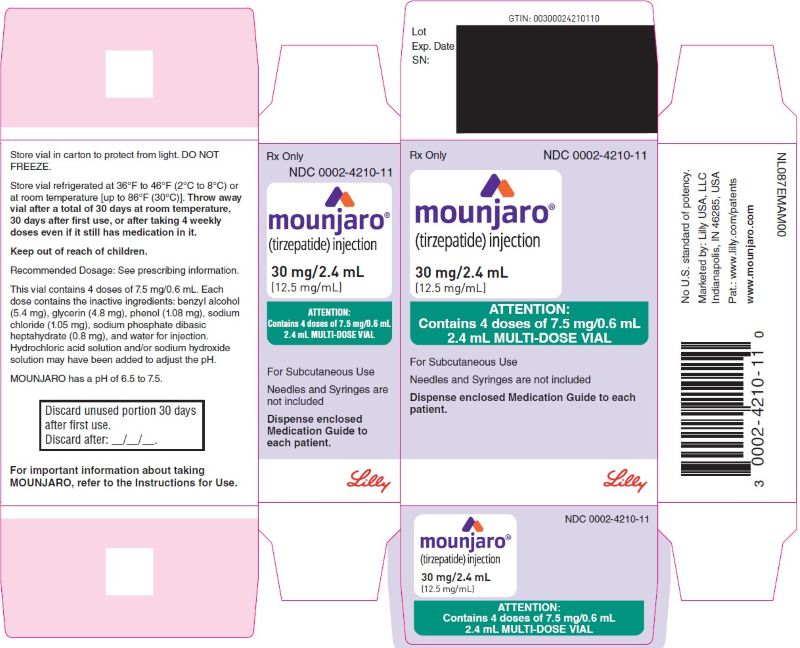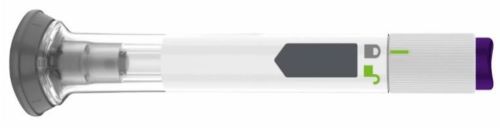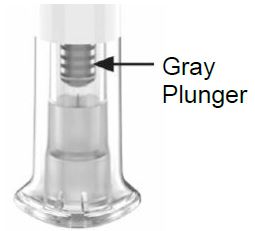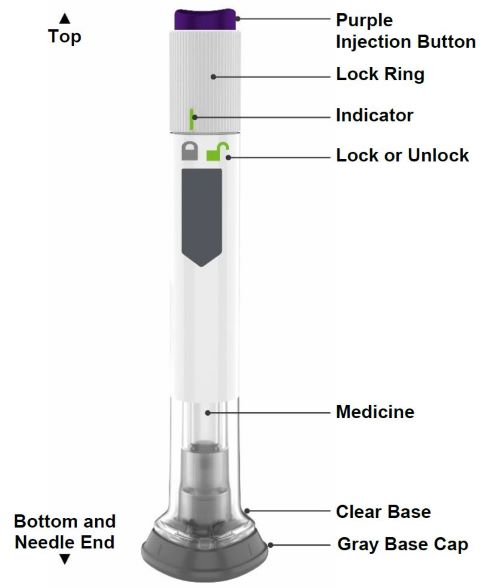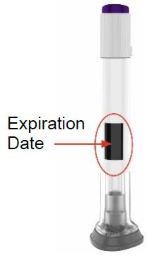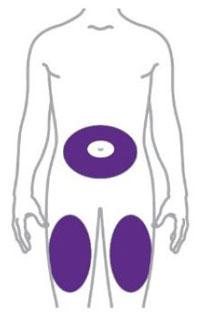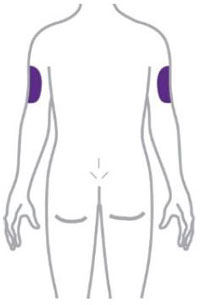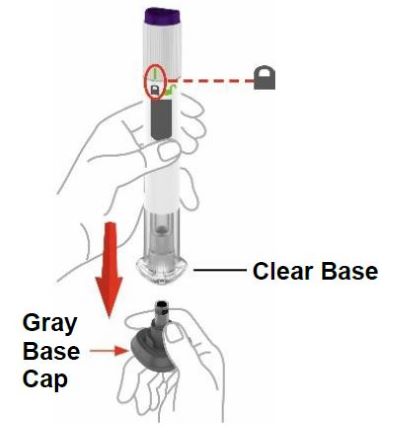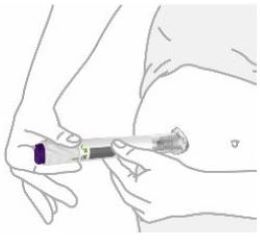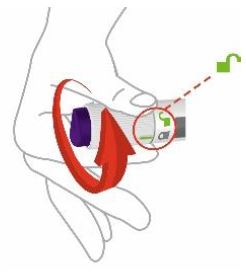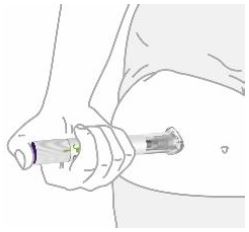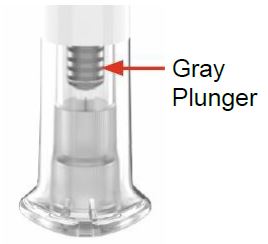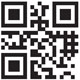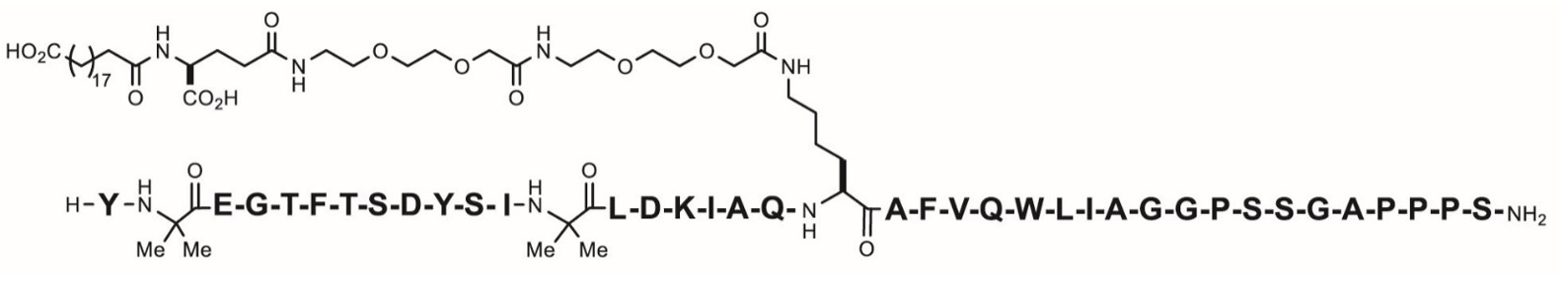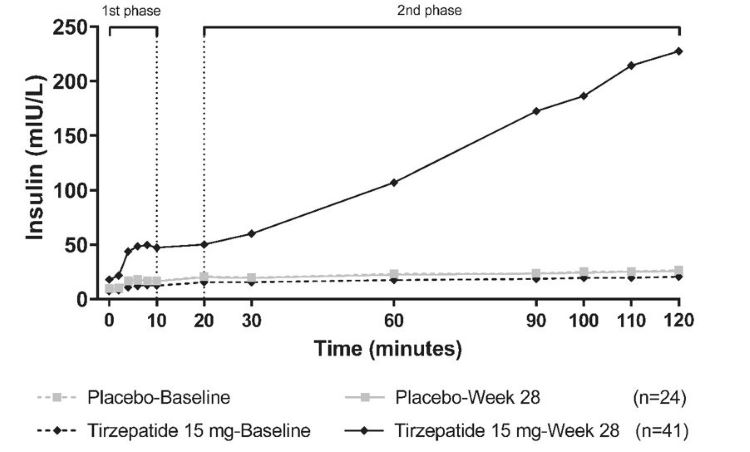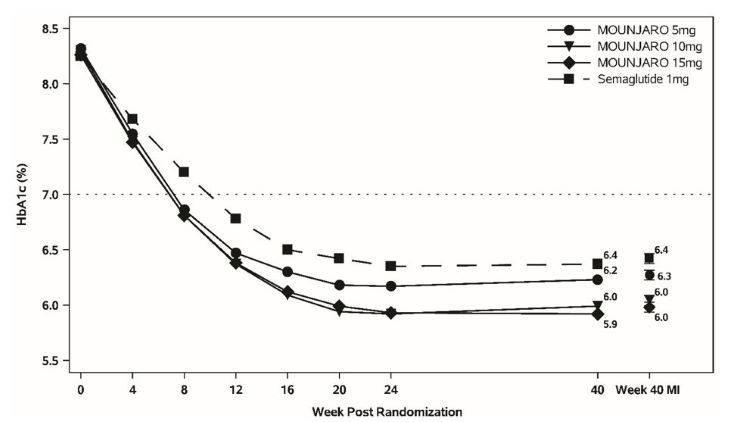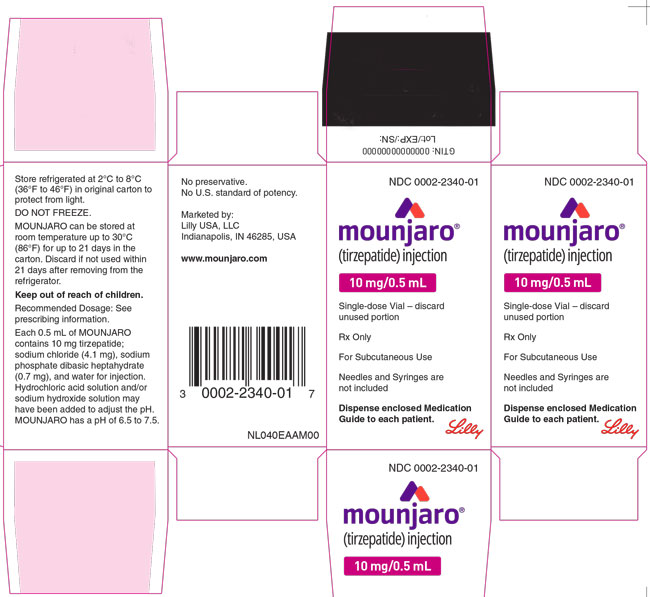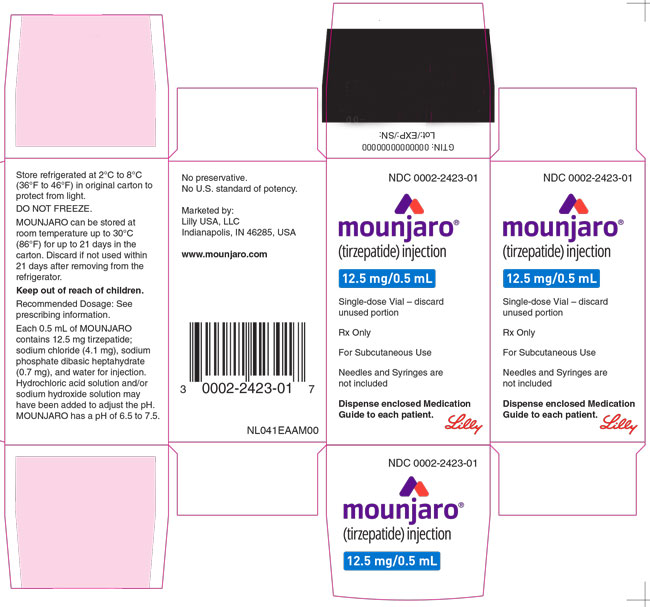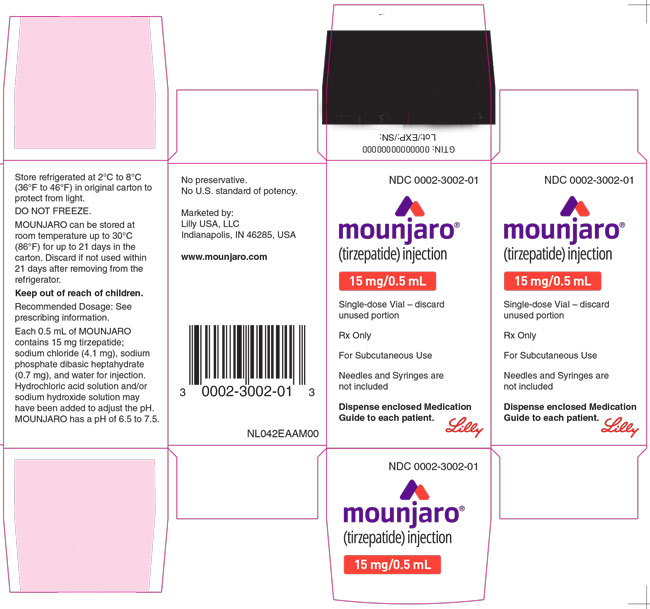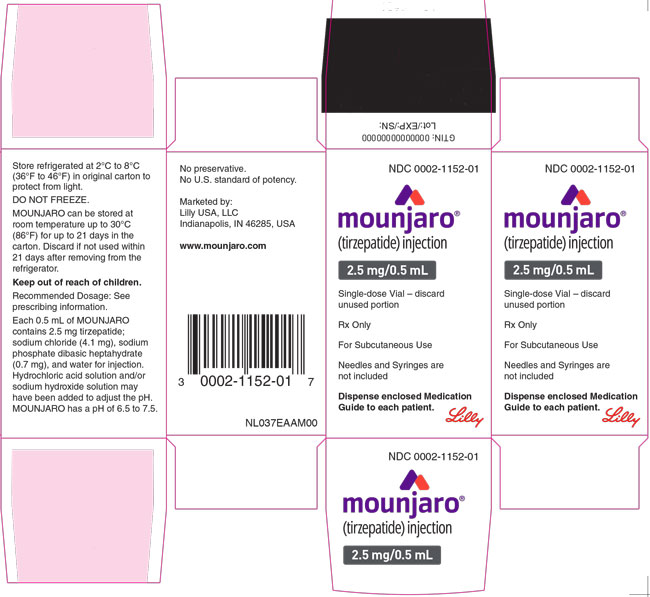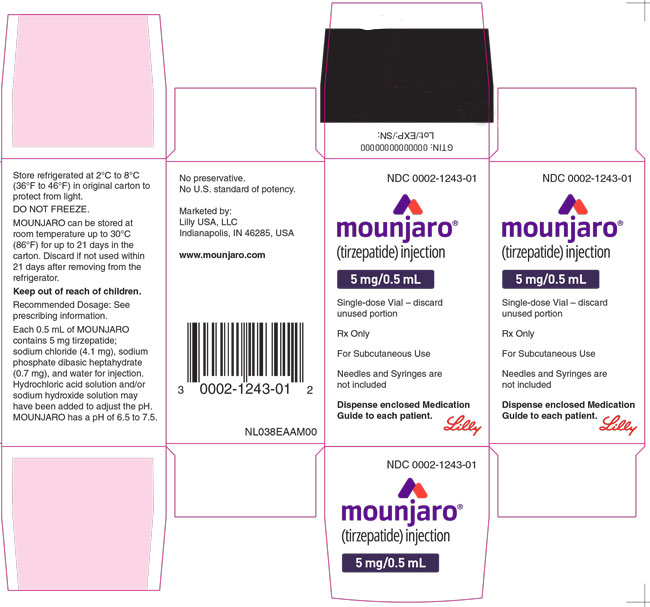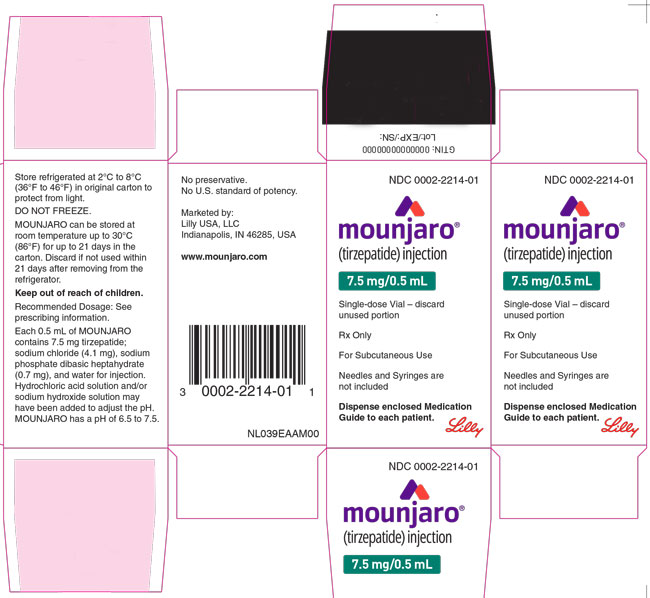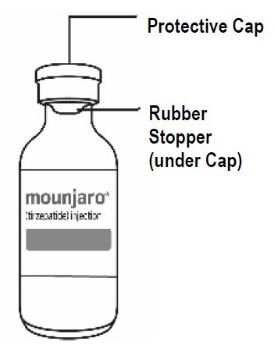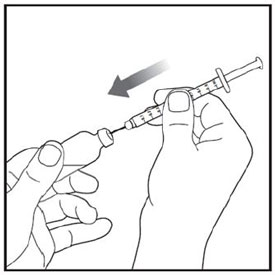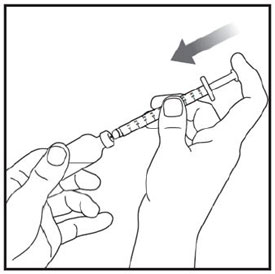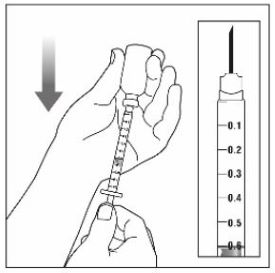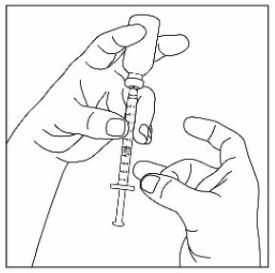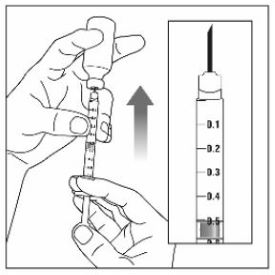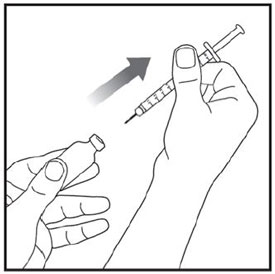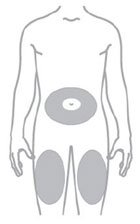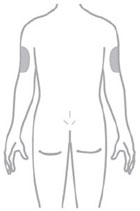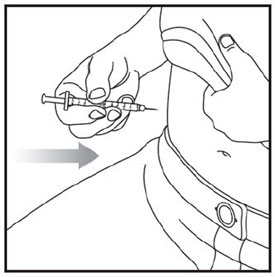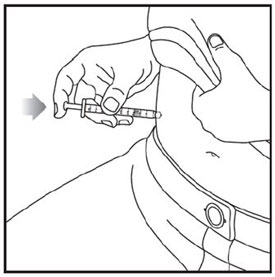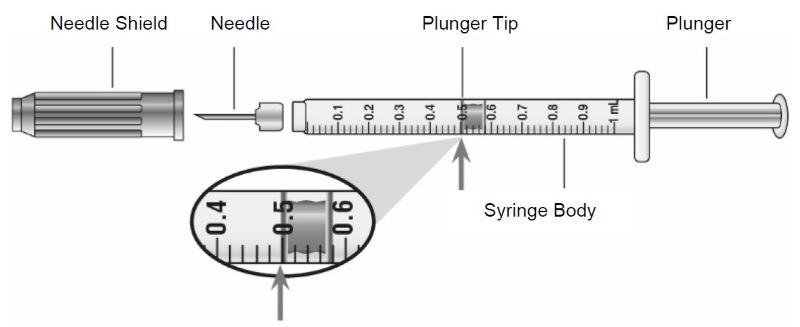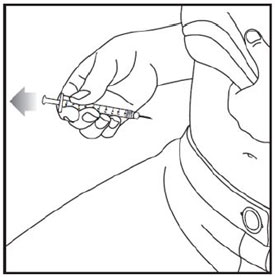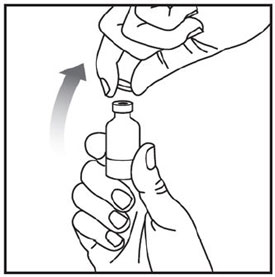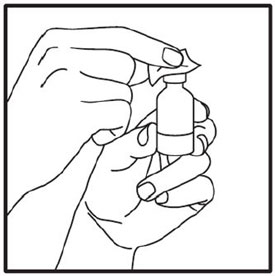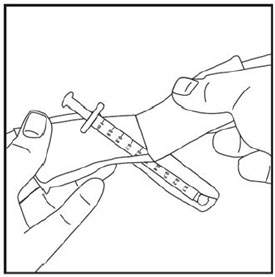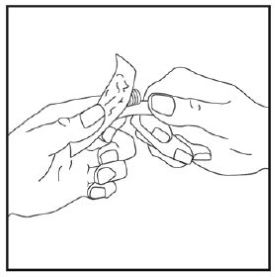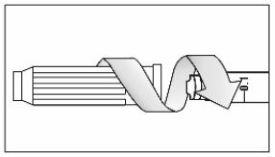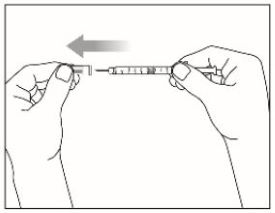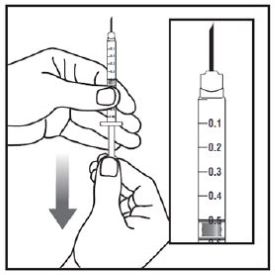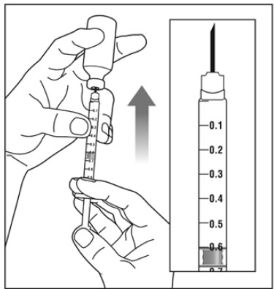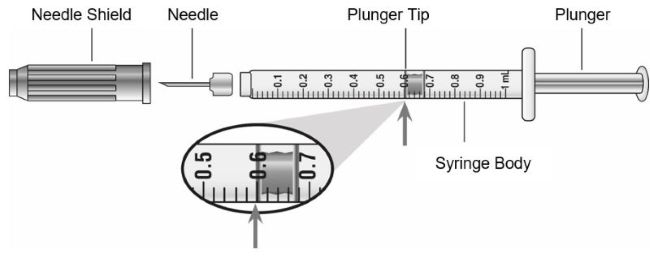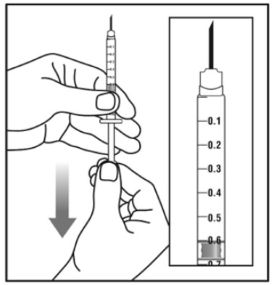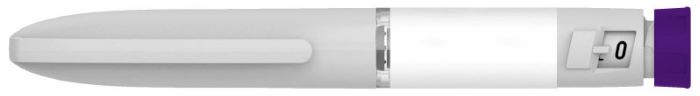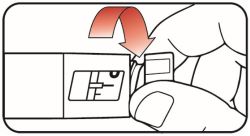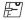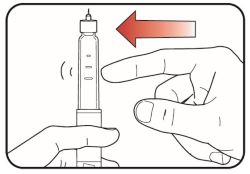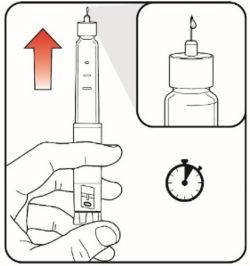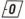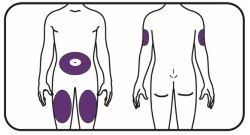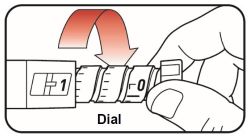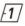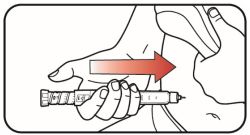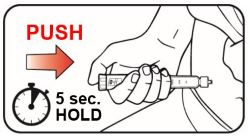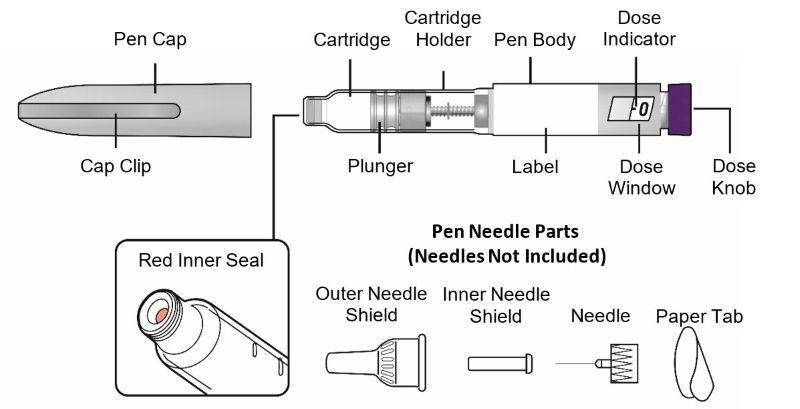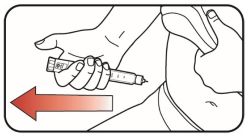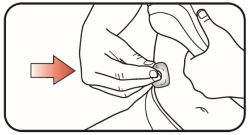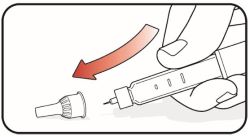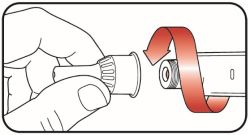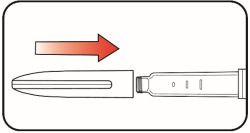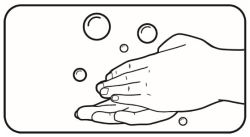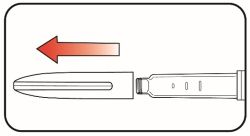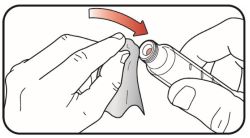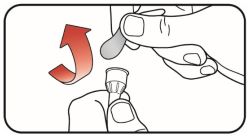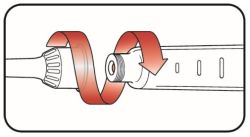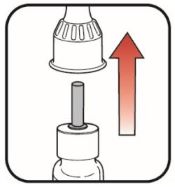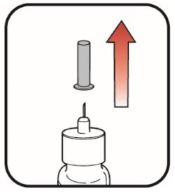 DRUG LABEL: Mounjaro
NDC: 0002-1506 | Form: INJECTION, SOLUTION
Manufacturer: Eli Lilly and Company
Category: prescription | Type: HUMAN PRESCRIPTION DRUG LABEL
Date: 20260121

ACTIVE INGREDIENTS: tirzepatide 2.5 mg/0.5 mL
INACTIVE INGREDIENTS: Sodium Phosphate, Dibasic, Heptahydrate 0.7 mg/0.5 mL; Sodium Chloride 4.1 mg/0.5 mL; Hydrochloric Acid; Sodium Hydroxide; Water

HIGHLIGHTS OF PRESCRIBING INFORMATION

These highlights do not include all the information needed to use MOUNJARO safely and effectively. See full prescribing information for MOUNJARO.
MOUNJARO® (tirzepatide) Injection, for subcutaneous use
Initial U.S. Approval: 2022

RECENT MAJOR CHANGES

Indications and Usage (1) | 12/2025
Dosage and Administration (2) Recommended Dosage (2.1) | 12/2025
Important Administration Instructions (2.2) | 01/2026
Warnings and Precautions
Severe Gastrointestinal Adverse Reactions (5.6) | 12/2025
Never Share a MOUNJARO KwikPen Between Patients (5.10) | 01/2026

WARNING: RISK OF THYROID C-CELL TUMORS

See full prescribing information for complete boxed warning.

- Tirzepatide causes thyroid C-cell tumors in rats. It is unknown whether MOUNJARO causes thyroid C-cell tumors, including medullary thyroid carcinoma (MTC), in humans as the human relevance of tirzepatide-induced rodent thyroid C-cell tumors has not been determined (5.1, 13.1).
- MOUNJARO is contraindicated in patients with a personal or family history of MTC or in patients with Multiple Endocrine Neoplasia syndrome type 2 (MEN 2). Counsel patients regarding the potential risk of MTC and symptoms of thyroid tumors (4, 5.1).

1 INDICATIONS AND USAGE

MOUNJARO® is a glucose-dependent insulinotropic polypeptide (GIP) receptor and glucagon-like peptide-1 (GLP-1) receptor agonist indicated as an adjunct to diet and exercise to improve glycemic control in adults and pediatric patients 10 years of age and older with type 2 diabetes mellitus. (1)

2 DOSAGE AND ADMINISTRATION

- The recommended starting dosage is 2.5 mg injected subcutaneously once weekly. (2.1)
- After 4 weeks, increase to 5 mg injected subcutaneously once weekly. (2.1)
- If additional glycemic control is needed, increase the dosage in 2.5 mg increments after at least 4 weeks on the current dose. (2.1)
- Maximum dosage (2.1):
  - Adults: 15 mg subcutaneously once weekly.
  - Pediatric patients 10 years of age and older: 10 mg subcutaneously once weekly.
- Administer once weekly at any time of day, with or without meals. (2.2)
- Inject subcutaneously in the abdomen, thigh, or another person should inject in the back of the upper arm. Rotate injection sites with each dose. (2.2)
- Refer to the Full Prescribing Information for additional important administration instructions about MOUNJARO presentations. (2.2)

3 DOSAGE FORMS AND STRENGTHS

Injection: 2.5 mg, 5 mg, 7.5 mg, 10 mg, 12.5 mg, or 15 mg per 0.5 mL in single-dose pen or single-dose vial (3)

Injection: 10 mg/2.4 mL (4.17 mg/mL) for four 2.5 mg/0.6 mL doses, 20 mg/2.4 mL (8.33 mg/mL) for four 5 mg/0.6 mL doses, 30 mg/2.4 mL (12.5 mg/mL) for four 7.5 mg/0.6 mL doses, 40 mg/2.4 mL (16.7 mg/mL) for four 10 mg/0.6 mL doses, 50 mg/2.4 mL (20.8 mg/mL) for four 12.5 mg/0.6 mL doses, or 60 mg/2.4 mL (25 mg/mL) for four 15 mg/0.6 mL doses in a multi-dose vial or single-patient-use KwikPen® (3)

4 CONTRAINDICATIONS

- Personal or family history of medullary thyroid carcinoma or in patients with Multiple Endocrine Neoplasia syndrome type 2. (4)
- Known serious hypersensitivity to tirzepatide or any of the excipients in MOUNJARO. (4)

5 WARNINGS AND PRECAUTIONS

- Acute Pancreatitis: Has been observed in patients treated with GLP-1 receptor agonists, or MOUNJARO. Discontinue if pancreatitis is suspected. (5.2)
- Hypoglycemia with Concomitant Use of Insulin Secretagogues or Insulin: Concomitant use with an insulin secretagogue or insulin may increase the risk of hypoglycemia, including severe hypoglycemia. Reducing dose of insulin secretagogue or insulin may be necessary. (5.3)
- Hypersensitivity Reactions: Serious hypersensitivity reactions (e.g., anaphylaxis and angioedema) have been reported. Discontinue MOUNJARO if suspected and promptly seek medical advice. (5.4)
- Acute Kidney Injury Due to Volume Depletion: Monitor renal function in patients reporting adverse reactions that could lead to volume depletion. (5.5)
- Severe Gastrointestinal Adverse Reactions: Use has been associated with gastrointestinal adverse reactions, sometimes severe. MOUNJARO is not recommended in patients with severe gastroparesis. (5.6)
- Diabetic Retinopathy Complications in Patients with a History of Diabetic Retinopathy: Has not been studied in patients with non-proliferative diabetic retinopathy requiring acute therapy, proliferative diabetic retinopathy, or diabetic macular edema. Monitor patients with a history of diabetic retinopathy for progression. (5.7)
- Acute Gallbladder Disease: Has occurred in clinical trials. If cholelithiasis is suspected, gallbladder studies and clinical follow-up are indicated. (5.8)
- Pulmonary Aspiration During General Anesthesia or Deep Sedation: Has been reported in patients receiving GLP-1 receptor agonists undergoing elective surgeries or procedures. Instruct patients to inform healthcare providers of any planned surgeries or procedures. (5.9)
- Never share a MOUNJARO KwikPen between patients, even if the pen needle is changed. (5.10)

6 ADVERSE REACTIONS

The most common adverse reactions, reported in ≥5% of patients treated with MOUNJARO are nausea, diarrhea, decreased appetite, vomiting, constipation, dyspepsia, and abdominal pain. (6.1)

To report SUSPECTED ADVERSE REACTIONS, contact Eli Lilly and Company at 1-800-LillyRx (1-800-545-5979) or FDA at 1-800-FDA-1088 or www.fda.gov/medwatch.

7 DRUG INTERACTIONS

MOUNJARO delays gastric emptying and has the potential to impact the absorption of concomitantly administered oral medications. (7.2)

8 USE IN SPECIFIC POPULATIONS

- Pregnancy: Based on animal studies, may cause fetal harm. (8.1)
- Females of Reproductive Potential: Advise females using oral contraceptives to switch to a non-oral contraceptive method or add a barrier method of contraception for 4 weeks after initiation and for 4 weeks after each dose escalation. (8.3)

FULL PRESCRIBING INFORMATION

WARNING: RISK OF THYROID C-CELL TUMORS

- In both male and female rats, tirzepatide causes dose-dependent and treatment-duration-dependent thyroid C-cell tumors at clinically relevant exposures. It is unknown whether MOUNJARO causes thyroid C-cell tumors, including medullary thyroid carcinoma (MTC), in humans as human relevance of tirzepatide-induced rodent thyroid C-cell tumors has not been determined [see Warnings and Precautions (5.1) and Nonclinical Toxicology (13.1)].
- MOUNJARO is contraindicated in patients with a personal or family history of MTC or in patients with Multiple Endocrine Neoplasia syndrome type 2 (MEN 2) [see Contraindications (4)]. Counsel patients regarding the potential risk for MTC with the use of MOUNJARO and inform them of symptoms of thyroid tumors (e.g., a mass in the neck, dysphagia, dyspnea, persistent hoarseness). Routine monitoring of serum calcitonin or using thyroid ultrasound is of uncertain value for early detection of MTC in patients treated with MOUNJARO [see Contraindications (4) and Warnings and Precautions (5.1)].

1 INDICATIONS AND USAGE

MOUNJARO® is indicated as an adjunct to diet and exercise to improve glycemic control in adults and pediatric patients 10 years of age and older with type 2 diabetes mellitus.

2 DOSAGE AND ADMINISTRATION

2.1 Recommended Dosage

- The recommended starting dosage of MOUNJARO is 2.5 mg injected subcutaneously once weekly [see Dosage and Administration (2.2)]. Follow the dosage escalation below to reduce the risk of gastrointestinal adverse reactions [see Warnings and Precautions (5.6) and Adverse Reactions (6.1)]. The 2.5 mg dosage is for treatment initiation and is not intended for glycemic control.
- After 4 weeks, increase the dosage to 5 mg injected subcutaneously once weekly.
- If additional glycemic control is needed, increase the dosage in 2.5 mg increments after at least 4 weeks on the current dose. The maximum dosage of MOUNJARO is:
  - 15 mg injected subcutaneously once weekly in adults.
  - 10 mg injected subcutaneously once weekly in pediatric patients.
- If a dose is missed, instruct patients to administer MOUNJARO as soon as possible within 4 days (96 hours) after the missed dose. If more than 4 days have passed, skip the missed dose and administer the next dose on the regularly scheduled day. In each case, patients can then resume their regular once weekly dosing schedule.
- The day of weekly administration can be changed, if necessary, as long as the time between the two doses is at least 3 days (72 hours).

2.2 Important Administration Instructions

- Inform patients and their caregiver(s) which MOUNJARO presentation (e.g., vial, pre-filled single-dose pen, single-patient-use KwikPen) they will receive and ensure they receive training appropriate for that specific presentation. If the prescribed MOUNJARO presentation changes, ensure patients and caregivers receive appropriate training and instruct them to consult the Instructions for Use for the newly prescribed presentation.
- Prior to initiation, train patients and their caregiver(s) on proper injection technique for the prescribed MOUNJARO presentation [see Instructions for Use]. After training, a patient may self-inject MOUNJARO if the healthcare provider determines that it can be properly administered, except for the following:
  - MOUNJARO KwikPen is not recommended for self-administration by pediatric patients.
  - MOUNJARO KwikPen is not recommended for self-administration by those who are visually impaired.
- Instruct patients using MOUNJARO vials to use a syringe appropriate for dose administration (e.g., a 1 mL syringe capable of measuring a 0.5 mL or 0.6 mL dose) and always use a new syringe and needle for each injection.
- Administer MOUNJARO once weekly, any time of day, with or without meals.
- Inject MOUNJARO subcutaneously in the abdomen, thigh, or another person should inject in the back of the upper arm.
- Rotate injection sites with each dose.
- Inspect MOUNJARO visually before use. It should appear clear and colorless to slightly yellow. Do not use MOUNJARO if particulate matter or discoloration is seen.
- When using MOUNJARO with insulin, administer as separate injections and never mix. It is acceptable to inject MOUNJARO and insulin in the same body region, but the injections should not be adjacent to each other.

3 DOSAGE FORMS AND STRENGTHS

Injection: Clear, colorless to slightly yellow solution in pre-filled single-dose pens, single-dose vials, multi-dose vials, or single-patient-use KwikPens, each available in the following strengths. The multi-dose vials and single-patient-use KwikPen each contain 4 doses:

Single-dose Pen or Vial

2.5 mg/0.5 mL

5 mg/0.5 mL

7.5 mg/0.5 mL

10 mg/0.5 mL

12.5 mg/0.5 mL

15 mg/0.5 mL

Multi-dose Vial (4 doses per vial)
Dose per Injection | Total Strength per Total Volume | Strength per mL
2.5 mg/0.6 mL | 10 mg/2.4 mL | 4.17 mg/mL
5 mg/0.6 mL | 20 mg/2.4 mL | 8.33 mg/mL
7.5 mg/0.6 mL | 30 mg/2.4 mL | 12.5 mg/mL
10 mg/0.6 mL | 40 mg/2.4 mL | 16.7 mg/mL
12.5 mg/0.6 mL | 50 mg/2.4 mL | 20.8 mg/mL
15 mg/0.6 mL | 60 mg/2.4 mL | 25 mg/mL

Single-Patient-Use KwikPen (4 doses per KwikPen)
Dose per Injection | Total Strength per Total Volume | Strength per mL
2.5 mg | 10 mg/2.4 mL | 4.17 mg/mL
5 mg | 20 mg/2.4 mL | 8.33 mg/mL
7.5 mg | 30 mg/2.4 mL | 12.5 mg/mL
10 mg | 40 mg/2.4 mL | 16.7 mg/mL
12.5 mg | 50 mg/2.4 mL | 20.8 mg/mL
15 mg | 60 mg/2.4 mL | 25 mg/mL

4 CONTRAINDICATIONS

MOUNJARO is contraindicated in patients with:

- A personal or family history of medullary thyroid carcinoma (MTC) or in patients with Multiple Endocrine Neoplasia syndrome type 2 (MEN 2) [see Warnings and Precautions (5.1)].
- Known serious hypersensitivity to tirzepatide or any of the excipients in MOUNJARO. Serious hypersensitivity reactions, including anaphylaxis and angioedema, have been reported with MOUNJARO [see Warnings and Precautions (5.4)].

5 WARNINGS AND PRECAUTIONS

5.1 Risk of Thyroid C-Cell Tumors

In both sexes of rats, tirzepatide caused a dose-dependent and treatment-duration-dependent increase in the incidence of thyroid C-cell tumors (adenomas and carcinomas) in a 2-year study at clinically relevant plasma exposures [see Nonclinical Toxicology (13.1)]. It is unknown whether MOUNJARO causes thyroid C-cell tumors, including medullary thyroid carcinoma (MTC), in humans as human relevance of tirzepatide-induced rodent thyroid C-cell tumors has not been determined.

MOUNJARO is contraindicated in patients with a personal or family history of MTC or in patients with MEN 2. Counsel patients regarding the potential risk for MTC with the use of MOUNJARO and inform them of symptoms of thyroid tumors (e.g., a mass in the neck, dysphagia, dyspnea, persistent hoarseness).

Routine monitoring of serum calcitonin or using thyroid ultrasound is of uncertain value for early detection of MTC in patients treated with MOUNJARO. Such monitoring may increase the risk of unnecessary procedures, due to the low test specificity for serum calcitonin and a high background incidence of thyroid disease. Significantly elevated serum calcitonin values may indicate MTC and patients with MTC usually have calcitonin values >50 ng/L. If serum calcitonin is measured and found to be elevated, the patient should be further evaluated. Patients with thyroid nodules noted on physical examination or neck imaging should also be further evaluated.

5.2 Acute Pancreatitis

Acute pancreatitis, including fatal and non-fatal hemorrhagic or necrotizing pancreatitis, has been observed in patients treated with GLP-1 receptor agonists, or MOUNJARO [see Adverse Reactions (6)].

After initiation of MOUNJARO, observe patients carefully for signs and symptoms of acute pancreatitis, which may include persistent or severe abdominal pain (sometimes radiating to the back) and which may or may not be accompanied by nausea or vomiting. If pancreatitis is suspected, discontinue MOUNJARO and initiate appropriate management.

5.3 Hypoglycemia with Concomitant Use of Insulin Secretagogues or Insulin

Patients receiving MOUNJARO in combination with an insulin secretagogue (e.g., sulfonylurea) or insulin may have an increased risk of hypoglycemia, including severe hypoglycemia [see Adverse Reactions (6.1), Drug Interactions (7.1)].

The risk of hypoglycemia may be lowered by a reduction in the dose of sulfonylurea (or other concomitantly administered insulin secretagogue) or insulin. Inform patients using these concomitant medications of the risk of hypoglycemia and educate them on the signs and symptoms of hypoglycemia.

5.4 Hypersensitivity Reactions

Serious hypersensitivity reactions (e.g., anaphylaxis, angioedema) have been reported in patients treated with MOUNJARO. If hypersensitivity reactions occur, discontinue use of MOUNJARO; treat promptly per standard of care, and monitor until signs and symptoms resolve. Do not use in patients with a previous serious hypersensitivity reaction to tirzepatide or any of the excipients in MOUNJARO [see Contraindications (4), Adverse Reactions (6.2)].

Anaphylaxis and angioedema have been reported with GLP-1 receptor agonists. Use caution in patients with a history of angioedema or anaphylaxis with a GLP-1 receptor agonist because it is unknown whether such patients will be predisposed to these reactions with MOUNJARO.

5.5 Acute Kidney Injury Due to Volume Depletion

There have been postmarketing reports of acute kidney injury, in some cases requiring hemodialysis, in patients treated with GLP-1 receptor agonists, or MOUNJARO. The majority of the reported events occurred in patients who experienced gastrointestinal adverse reactions leading to dehydration such as nausea, vomiting, or diarrhea [see Adverse Reactions (6)].

Monitor renal function in patients reporting adverse reactions to MOUNJARO that could lead to volume depletion, especially during dosage initiation and escalation of MOUNJARO.

5.6 Severe Gastrointestinal Adverse Reactions

Use of MOUNJARO has been associated with gastrointestinal adverse reactions, sometimes severe [see Adverse Reactions (6)]. In the pool of placebo-controlled trials in adults, severe gastrointestinal adverse reactions occurred more frequently among patients receiving MOUNJARO (5 mg 1.3%, 10 mg 0.4%, 15 mg 1.2%) than placebo (0.9%). Severe gastrointestinal adverse reactions have also been reported postmarketing with GLP-1 receptor agonists.

MOUNJARO is not recommended in patients with severe gastroparesis.

5.7 Diabetic Retinopathy Complications in Patients with a History of Diabetic Retinopathy

Rapid improvement in glucose control has been associated with a temporary worsening of diabetic retinopathy. MOUNJARO has not been studied in patients with non-proliferative diabetic retinopathy requiring acute therapy, proliferative diabetic retinopathy, or diabetic macular edema. Patients with a history of diabetic retinopathy should be monitored for progression of diabetic retinopathy.

5.8 Acute Gallbladder Disease

Acute events of gallbladder disease such as cholelithiasis or cholecystitis have been reported in GLP-1 receptor agonist trials and postmarketing.

In MOUNJARO placebo-controlled clinical trials in adults, acute gallbladder disease (cholelithiasis, biliary colic, and cholecystectomy) was reported by 0.6% of MOUNJARO-treated patients and 0% of placebo-treated patients. If cholelithiasis is suspected, gallbladder diagnostic studies and appropriate clinical follow-up are indicated.

5.9 Pulmonary Aspiration During General Anesthesia or Deep Sedation

MOUNJARO delays gastric emptying [see Clinical Pharmacology (12.2)]. There have been rare postmarketing reports of pulmonary aspiration in patients receiving GLP-1 receptor agonists undergoing elective surgeries or procedures requiring general anesthesia or deep sedation who had residual gastric contents despite reported adherence to preoperative fasting recommendations.

Available data are insufficient to inform recommendations to mitigate the risk of pulmonary aspiration during general anesthesia or deep sedation in patients taking MOUNJARO, including whether modifying preoperative fasting recommendations or temporarily discontinuing MOUNJARO could reduce the incidence of retained gastric contents. Instruct patients to inform healthcare providers prior to any planned surgeries or procedures if they are taking MOUNJARO.

5.10 Never Share a MOUNJARO KwikPen Between Patients

Never share MOUNJARO KwikPen between patients, even if the pen needle is changed. Sharing poses a risk for transmission of blood-borne pathogens.

6 ADVERSE REACTIONS

The following serious adverse reactions are described below or elsewhere in the prescribing information:

- Risk of Thyroid C-cell Tumors [see Warnings and Precautions (5.1)]
- Acute Pancreatitis [see Warnings and Precautions (5.2)]
- Hypoglycemia with Concomitant Use of Insulin Secretagogues or Insulin [see Warnings and Precautions (5.3)]
- Hypersensitivity Reactions [see Warnings and Precautions (5.4)]
- Acute Kidney Injury Due to Volume Depletion [see Warnings and Precautions (5.5)]
- Severe Gastrointestinal Adverse Reactions [see Warnings and Precautions (5.6)]
- Diabetic Retinopathy Complications in Patients with a History of Diabetic Retinopathy [see Warnings and Precautions (5.7)]
- Acute Gallbladder Disease [see Warnings and Precautions (5.8)]
- Pulmonary Aspiration During General Anesthesia or Deep Sedation [see Warnings and Precautions (5.9)]

6.1 Clinical Trials Experience

Because clinical trials are conducted under widely varying conditions, adverse reaction rates observed in the clinical trials of a drug cannot be directly compared to rates in the clinical trials of another drug and may not reflect the rates observed in practice.

Adverse Reactions in the Clinical Trials of Adults with Type 2 Diabetes Mellitus

Pool of Two Placebo-Controlled Clinical Trials in Adults

The data in Table 1 are derived from 2 placebo-controlled trials [1 monotherapy trial (SURPASS-1) and 1 trial in combination with basal insulin with or without metformin (SURPASS-5)] in adult patients with type 2 diabetes mellitus [see Clinical Studies (14.2, 14.4)]. These data reflect exposure of 718 patients to MOUNJARO and a mean duration of exposure to MOUNJARO of 36.6 weeks. The mean age of patients was 58 years, 4% were 75 years or older and 54% were male. The population was 57% White, 27% Asian, 13% American Indian or Alaska Native, and 3% Black or African American; 25% identified as Hispanic or Latino ethnicity. At baseline, patients had type 2 diabetes mellitus for an average of 9.1 years with a mean HbA1c of 8.1%. As assessed by baseline fundoscopic examination, 13% of the population had retinopathy. At baseline, eGFR was ≥90 mL/min/1.73 m^2 in 53%, 60 to 90 mL/min/1.73 m^2 in 39%, 45 to 60 mL/min/1.73 m^2 in 7%, and 30 to 45 mL/min/1.73 m^2 in 1% of patients.

Pool of Seven Controlled Clinical Trials

Adverse reactions were also evaluated in a larger pool of adult patients with type 2 diabetes mellitus participating in seven controlled clinical trials which included two placebo-controlled trials (SURPASS-1 and -5), three trials of MOUNJARO in combination with metformin, sulfonylureas, and/or SGLT2 Inhibitors (SURPASS-2, -3, -4) [see Clinical Studies (14.3)] and two additional trials conducted in Japan. In this pool, a total of 5119 adult patients with type 2 diabetes mellitus were treated with MOUNJARO for a mean duration of 48.1 weeks. The mean age of patients was 58 years, 4% were 75 years or older and 58% were male. The population was 65% White, 24% Asian, 7% American Indian or Alaska Native, and 3% Black or African American; 38% identified as Hispanic or Latino ethnicity. At baseline, patients had type 2 diabetes mellitus for an average of 9.1 years with a mean HbA1c of 8.3%. As assessed by baseline fundoscopic examination, 15% of the population had retinopathy. At baseline, eGFR was ≥90 mL/min/1.73 m^2 in 52%, 60 to 90 mL/min/1.73 m^2 in 40%, 45 to 60 mL/min/1.73 m^2 in 6%, and 30 to 45 mL/min/1.73 m^2 in 1% of patients.

Common Adverse Reactions

Table 1 shows common adverse reactions, not including hypoglycemia, associated with the use of MOUNJARO in the pool of placebo-controlled trials in adults. These adverse reactions occurred more commonly on MOUNJARO than on placebo and occurred in at least 5% of patients treated with MOUNJARO.

Table 1: Adverse Reactions in Pool of Placebo-Controlled Trials Reported in ≥5% of MOUNJARO-treated Adult Patients with Type 2 Diabetes Mellitus
Adverse Reaction | Placebo (N=235) % | MOUNJARO 5 mg (N=237) % | MOUNJARO 10 mg (N=240) % | MOUNJARO 15 mg (N=241) %
Nausea | 4 | 12 | 15 | 18
Diarrhea | 9 | 12 | 13 | 17
Decreased Appetite | 1 | 5 | 10 | 11
Vomiting | 2 | 5 | 5 | 9
Constipation | 1 | 6 | 6 | 7
Dyspepsia | 3 | 8 | 8 | 5
Abdominal Pain | 4 | 6 | 5 | 5
Note: Percentages reflect the number of patients who reported at least 1 occurrence of the adverse reaction.

In the pool of seven clinical trials in adults, the types and frequency of common adverse reactions, not including hypoglycemia, were similar to those listed in Table 1.

Gastrointestinal Adverse Reactions

In the pool of placebo-controlled trials in adults, gastrointestinal adverse reactions occurred more frequently among patients receiving MOUNJARO than placebo (placebo 20.4%, MOUNJARO 5 mg 37.1%, MOUNJARO 10 mg 39.6%, MOUNJARO 15 mg 43.6%). More patients receiving MOUNJARO 5 mg (3.0%), MOUNJARO 10 mg (5.4%), and MOUNJARO 15 mg (6.6%) discontinued treatment due to gastrointestinal adverse reactions than patients receiving placebo (0.4%). The majority of reports of nausea, vomiting, and/or diarrhea occurred during dose escalation and decreased over time.

The following gastrointestinal adverse reactions were reported more frequently in MOUNJARO-treated adult patients than placebo-treated patients (frequencies listed, respectively, as: placebo; 5 mg; 10 mg; 15 mg): eructation (0.4%, 3.0%, 2.5%, 3.3%), flatulence (0%, 1.3%, 2.5%, 2.9%), gastroesophageal reflux disease (0.4%, 1.7%, 2.5%, 1.7%), abdominal distension (0.4%, 0.4%, 2.9%, 0.8%).

Other Adverse Reactions in Adults

Hypoglycemia

Table 2 summarizes the incidence of hypoglycemic events in the placebo-controlled trials in adults.

Table 2: Hypoglycemia Adverse Reactions in Placebo-Controlled Trials in Adult Patients with Type 2 Diabetes Mellitus
 | Placebo % | MOUNJARO 5 mg % | MOUNJARO 10 mg % | MOUNJARO 15 mg %
Monotherapy
(40 weeks)* | N=115 | N=121 | N=119 | N=120
Blood glucose <54 mg/dL | 1 | 0 | 0 | 0
Severe hypoglycemia** | 0 | 0 | 0 | 0
Add-on to Basal Insulin with or without Metformin
(40 weeks)* | N=120 | N=116 | N=119 | N=120
Blood glucose <54 mg/dL | 13 | 16 | 19 | 14
Severe hypoglycemia** | 0 | 0 | 2 | 1
Note: Percentages reflect the number of patients who reported at least 1 episode of hypoglycemia in respective categories.
* Reflects the study treatment period. Data include events occurring during 4 weeks of treatment-free safety follow up. Events after introduction of a new glucose-lowering treatment are excluded.
** Episodes requiring the assistance of another person to actively administer carbohydrate, glucagon, or other resuscitative actions.

Hypoglycemia was more frequent when MOUNJARO was used in combination with a sulfonylurea [see Clinical Studies (14)]. In an adult clinical trial up to 104 weeks of treatment, when administered with a sulfonylurea, hypoglycemia (glucose level <54 mg/dL) occurred in 13.8%, 9.9%, and 12.8%, and severe hypoglycemia occurred in 0.5%, 0%, and 0.6% of patients treated with MOUNJARO 5 mg, 10 mg, and 15 mg, respectively.

Acute Pancreatitis

In clinical studies, 14 events of acute pancreatitis were confirmed by adjudication in 13 MOUNJARO-treated adult patients (0.23 patients per 100 years of exposure) versus 3 events in 3 comparator-treated patients (0.11 patients per 100 years of exposure).

Heart Rate Increase

In the pool of placebo-controlled trials, treatment of adults with MOUNJARO resulted in a mean increase in heart rate of 2 to 4 beats per minute compared to a mean increase of 1 beat per minute in placebo-treated patients. Episodes of sinus tachycardia, associated with a concomitant increase from baseline in heart rate of ≥15 beats per minute, also were reported in 4.3%, 4.6%, 5.9% and 10% of subjects treated with placebo, MOUNJARO 5 mg, 10 mg, and 15 mg, respectively. For patients enrolled in Japan, these episodes were reported in 7% (3/43), 7.1% (3/42), 9.3% (4/43), and 23% (10/43) of patients treated with placebo, MOUNJARO 5 mg, 10 mg, and 15 mg, respectively. The clinical relevance of heart rate increases is uncertain.

Hypersensitivity Reactions

Hypersensitivity reactions have been reported with MOUNJARO in the pool of placebo-controlled trials in adults, sometimes severe (e.g., urticaria and eczema); hypersensitivity reactions were reported in 3.2% of MOUNJARO-treated patients compared to 1.7% of placebo-treated patients.

In the pool of seven clinical trials in adults, hypersensitivity reactions occurred in 106/2,570 (4.1%) of MOUNJARO-treated adult patients with anti-tirzepatide antibodies and in 73/2,455 (3.0%) of MOUNJARO-treated patients who did not develop anti-tirzepatide antibodies. In the clinical trial in pediatric patients 10 years of age and older, hypersensitivity reactions occurred in 2/50 (4%) of MOUNJARO-treated pediatric patients with anti-tirzepatide antibodies and in 0/43 (0%) of MOUNJARO-treated pediatric patients who did not develop anti-tirzepatide antibodies [see Clinical Pharmacology (12.6)].

Injection Site Reactions

In the pool of placebo-controlled trials in adults, injection site reactions were reported in 3.2% of MOUNJARO-treated patients compared to 0.4% of placebo-treated patients.

In the pool of seven clinical trials, injection site reactions occurred in 119/2,570 (4.6%) of MOUNJARO-treated adult patients with anti-tirzepatide antibodies and in 18/2,455 (0.7%) of MOUNJARO-treated adult patients who did not develop anti-tirzepatide antibodies. In the clinical trial in pediatric patients 10 years of age and older, injection site reactions occurred in 3/50 (6%) of MOUNJARO-treated pediatric patients with anti-tirzepatide antibodies and in 0/43 (0%) of MOUNJARO-treated pediatric patients who did not develop anti-tirzepatide antibodies [see Clinical Pharmacology (12.6)].

Acute Gallbladder Disease

In the pool of placebo-controlled clinical trials in adults, acute gallbladder disease (cholelithiasis, biliary colic and cholecystectomy) was reported by 0.6% of MOUNJARO-treated patients and 0% of placebo-treated patients.

Dysesthesia

In the pool of placebo-controlled clinical trials in adults, dysesthesia was reported by 0.4%, 0.4%, and 0.4% of patients treated with MOUNJARO 5 mg, 10 mg, and 15 mg, respectively. No events were reported by patients receiving placebo.

Dysgeusia

In the pool of placebo-controlled clinical trials in adults, dysgeusia was reported by 0.1% of MOUNJARO-treated patients and 0% of placebo-treated patients.

Laboratory Abnormalities

Amylase and Lipase Increase

In the pool of placebo-controlled adult clinical trials, treatment with MOUNJARO resulted in mean increases from baseline in serum pancreatic amylase concentrations of 33% to 38% and serum lipase concentrations of 31% to 42%. Placebo-treated patients had a mean increase from baseline in pancreatic amylase of 4% and no changes were observed in lipase. The clinical significance of elevations in lipase or amylase with MOUNJARO is unknown in the absence of other signs and symptoms of pancreatitis.

Adverse Reactions in the Clinical Trial of Pediatric Patients 10 Years of Age and Older with Type 2 Diabetes Mellitus

MOUNJARO was administered to 97 pediatric patients 10 years of age and older with type 2 diabetes mellitus for a mean duration of 39.9 weeks [see Clinical Studies (14.5)]. The mean age was 15 years and 61% of patients were female. The population was 58% White, 11% Black or African American, 6% Asian, 20% American Indian or Alaska Native, and 5% were other races; 66% identified as Hispanic or Latino ethnicity. At baseline, pediatric patients had type 2 diabetes mellitus for an average of 2.4 years with a mean HbA1c of 8.0%.

The incidences of adverse reactions reported in pediatric patients treated with MOUNJARO 5 mg and 10 mg subcutaneously once-weekly were consistent with those described above for adult patients with type 2 diabetes mellitus with the exception of a higher incidence of vomiting, abdominal pain, and hypoglycemia. During the 30-week placebo-controlled period of the study, vomiting occurred in 3%, 16%, and 12% of patients and abdominal pain occurred in 9%, 22%, and 15% of patients treated with placebo, MOUNJARO 5 mg, and 10 mg, respectively.

No severe hypoglycemia episodes were reported during the trial. Table 3 summarizes the incidence of hypoglycemic events with blood glucose <54 mg/dL in the trial.

Table 3: Hypoglycemia Adverse Reactions in the 30 Week Trial of MOUNJARO Added to Metformin or Basal Insulin, or Both in Pediatric Patients 10 Years of Age and Older with Type 2 Diabetes Mellitus
 | Placebo % | MOUNJARO 5 mg % | MOUNJARO 10 mg %
Add on to basal insulin with or without metformina | N=10 | N=10 | N=11
Blood glucose <54 mg/dL | 10 | 30 | 27
Add on to metformin alonea | N=24 | N=22 | N=22
Blood glucose <54 mg/dL | 4 | 9 | 9
Note: Percentages reflect the number of patients who reported at least 1 episode of blood glucose <54 mg/dL.
a Events after the introduction of a new glucose-lowering treatment are excluded.

6.2 Postmarketing Experience

The following adverse reactions have been reported during post-approval use of MOUNJARO. Because these reactions are reported voluntarily from a population of uncertain size, it is not always possible to reliably estimate their frequency or establish a causal relationship to drug exposure.

Hypersensitivity: anaphylaxis, angioedema

Gastrointestinal: acute pancreatitis, hemorrhagic and necrotizing pancreatitis sometimes resulting in death, ileus, intestinal obstruction, severe constipation including fecal impaction

Pulmonary: Pulmonary aspiration has occurred in patients receiving GLP-1 receptor agonists undergoing elective surgeries or procedures requiring general anesthesia or deep sedation

Renal: acute renal failure or worsening of chronic renal failure, sometimes requiring hemodialysis

Skin and Subcutaneous Tissue: alopecia

7 DRUG INTERACTIONS

7.1 Concomitant Use with an Insulin Secretagogue (e.g., Sulfonylurea) or with Insulin

When initiating MOUNJARO, consider reducing the dose of concomitantly administered insulin secretagogues (e.g., sulfonylureas) or insulin to reduce the risk of hypoglycemia [see Warnings and Precautions (5.3)].

7.2 Oral Medications

MOUNJARO delays gastric emptying and thereby has the potential to impact the absorption of concomitantly administered oral medications. Caution should be exercised when oral medications are concomitantly administered with MOUNJARO.

Monitor patients on oral medications dependent on threshold concentrations for efficacy and those with a narrow therapeutic index (e.g., warfarin) when concomitantly administered with MOUNJARO.

Advise patients using oral hormonal contraceptives to switch to a non-oral contraceptive method or add a barrier method of contraception for 4 weeks after initiation and for 4 weeks after each dose escalation with MOUNJARO. Hormonal contraceptives that are not administered orally should not be affected [see Use in Specific Populations (8.3) and Clinical Pharmacology (12.2, 12.3)].

8 USE IN SPECIFIC POPULATIONS

8.1 Pregnancy

Risk Summary

Available data with MOUNJARO use in pregnant women are insufficient to evaluate for a drug-related risk of major birth defects, miscarriage, or other adverse maternal or fetal outcomes. There are risks to the mother and fetus associated with poorly controlled diabetes in pregnancy (see Clinical Considerations). Based on animal reproduction studies, there may be risks to the fetus from exposure to tirzepatide during pregnancy. MOUNJARO should be used during pregnancy only if the potential benefit justifies the potential risk to the fetus.

In pregnant rats administered tirzepatide during organogenesis, fetal growth reductions and fetal abnormalities occurred at clinical exposure in maternal rats based on AUC. In rabbits administered tirzepatide during organogenesis, fetal growth reductions were observed at clinically relevant exposures based on AUC. These adverse embryo/fetal effects in animals coincided with pharmacological effects on maternal weight and food consumption (see Data).

The estimated background risk of major birth defects is 6–10% in women with pre-gestational diabetes with an HbA1c >7% and has been reported to be as high as 20–25% in women with an HbA1c >10%. The estimated background risk of miscarriage for the indicated population is unknown. In the U.S. general population, the estimated background risk of major birth defects and miscarriage in clinically recognized pregnancies is 2–4% and 15–20%, respectively.

Clinical Considerations

Disease-Associated Maternal and/or Embryo/Fetal Risk

Poorly controlled diabetes in pregnancy increases the maternal risk for diabetic ketoacidosis, pre-eclampsia, spontaneous abortions, preterm delivery, and delivery complications. Poorly controlled diabetes increases the fetal risk for major birth defects, stillbirth, and macrosomia-related morbidity.

Data

Animal Data

In pregnant rats given twice weekly subcutaneous doses of 0.02, 0.1, and 0.5 mg/kg tirzepatide (0.03-, 0.07-, and 0.5-fold the MRHD of 15 mg once weekly based on AUC) during organogenesis, increased incidences of external, visceral, and skeletal malformations, increased incidences of visceral and skeletal developmental variations, and decreased fetal weights coincided with pharmacologically-mediated reductions in maternal body weights and food consumption at 0.5 mg/kg. In pregnant rabbits given once weekly subcutaneous doses of 0.01, 0.03, or 0.1 mg/kg tirzepatide (0.01-, 0.06-, and 0.2-fold the MRHD) during organogenesis, pharmacologically-mediated effects on the gastrointestinal system resulting in maternal mortality or abortion in a few rabbits occurred at all dose levels. Reduced fetal weights associated with decreased maternal food consumption and body weights were observed at 0.1 mg/kg. In a pre- and post-natal study in rats administered subcutaneous doses of 0.02, 0.10, or 0.25 mg/kg tirzepatide twice weekly from implantation through lactation, F1 pups from F0 maternal rats given 0.25 mg/kg tirzepatide had statistically significant lower mean body weight when compared to controls from post-natal day 7 through post-natal day 126 for males and post-natal day 56 for females.

8.2 Lactation

Risk Summary

In a single-dose clinical lactation study, the concentration of tirzepatide in breast milk was found to be either undetectable or low compared to the maternal administered dose (see Data). There are no available data on the effects of tirzepatide on the breastfed infant or on milk production. The developmental and health benefits of breastfeeding should be considered along with the mother's clinical need for MOUNJARO and any potential adverse effects on the breastfed infant from MOUNJARO or from the underlying maternal condition.

Data

Following subcutaneous administration of a single 5 mg dose to 11 healthy lactating adult females, the concentration of tirzepatide in breast milk was found to be undetectable (limit of detection in breast milk 4 ng/mL) in 164/171 samples assayed. The cumulative amount of tirzepatide detected in the remaining 7 breast milk samples over the 28-day sampling window was equivalent to less than 0.02% of the maternal administered dose, with the last measurable concentrations occurring 5 days post-dose. The AUC of tirzepatide in breast milk could not be calculated, due to insufficient quantifiable concentrations.

8.3 Females and Males of Reproductive Potential

Contraception

Use of MOUNJARO may reduce the efficacy of oral hormonal contraceptives due to delayed gastric emptying. This delay is largest after the first dose and diminishes over time. Advise patients using oral hormonal contraceptives to switch to a non-oral contraceptive method or add a barrier method of contraception for 4 weeks after initiation and for 4 weeks after each dose escalation with MOUNJARO [see Drug Interactions (7.2) and Clinical Pharmacology (12.2, 12.3)].

8.4 Pediatric Use

The safety and effectiveness of MOUNJARO as an adjunct to diet and exercise to improve glycemic control in pediatric patients 10 years of age and older with type 2 diabetes mellitus have been established. Use of MOUNJARO for this indication is supported by a 30-week, randomized, double-blind, placebo-controlled trial with a 22-week open label extension in 99 pediatric patients [see Clinical Studies (14.5)].

Adverse reactions reported in pediatric patients 10 years of age and older treated with MOUNJARO were similar to those reported in adults with the exception of a higher incidence of vomiting, abdominal pain, and hypoglycemia [see Adverse Reactions (6.1)].

The safety and effectiveness of MOUNJARO have not been established in pediatric patients less than 10 years of age.

8.5 Geriatric Use

In the pool of seven clinical trials, 1539 (30.1%) MOUNJARO-treated patients were 65 years of age or older, and 212 (4.1%) MOUNJARO-treated patients were 75 years of age or older at baseline.

No overall differences in safety or efficacy were detected between these patients and younger patients, but greater sensitivity of some older individuals cannot be ruled out.

8.6 Renal Impairment

No dosage adjustment of MOUNJARO is recommended for patients with renal impairment. In subjects with renal impairment including end-stage renal disease (ESRD), no change in tirzepatide pharmacokinetics (PK) was observed [see Clinical Pharmacology (12.3)]. Monitor renal function when initiating or escalating doses of MOUNJARO in patients with renal impairment reporting severe adverse gastrointestinal reactions [see Warnings and Precautions (5.5)].

8.7 Hepatic Impairment

No dosage adjustment of MOUNJARO is recommended for patients with hepatic impairment. In a clinical pharmacology study in subjects with varying degrees of hepatic impairment, no change in tirzepatide PK was observed [see Clinical Pharmacology (12.3)].

10 OVERDOSAGE

In the event of an overdosage, consider contacting the Poison Help line (1-800-222-1222) or a medical toxicologist for additional overdosage management recommendations. Initiate appropriate supportive treatment according to the patient's clinical signs and symptoms. A period of observation and treatment for these symptoms may be necessary, taking into account the half-life of tirzepatide of approximately 5 days.

11 DESCRIPTION

MOUNJARO (tirzepatide) injection, for subcutaneous use, contains tirzepatide, a once weekly GIP receptor and GLP-1 receptor agonist. Tirzepatide is based on the GIP sequence and contains aminoisobutyric acid (Aib) in positions 2 and 13, a C-terminal amide, and Lys residue at position 20 that is attached to 1,20-eicosanedioic acid via a linker. The molecular weight is 4813.53 Da and the empirical formula is C225H348N48O68.

Structural formula:

MOUNJARO is a clear, colorless to slightly yellow, sterile solution for subcutaneous use. Each single-dose pen or single-dose vial contains a 0.5 mL solution of 2.5 mg, 5 mg, 7.5 mg, 10 mg, 12.5 mg, or 15 mg of tirzepatide and the following excipients: sodium chloride (4.1 mg), sodium phosphate dibasic heptahydrate (0.7 mg), and water for injection. Each multi-dose vial or single-patient-use KwikPen contains 2.4 mL of solution, which provides 4 doses of 2.5 mg, 5 mg, 7.5 mg, 10 mg, 12.5 mg, or 15 mg of tirzepatide per 0.6 mL. Each dose contains the following excipients: benzyl alcohol (5.4 mg), glycerin (4.8 mg), phenol (1.08 mg), sodium chloride (1.05 mg), sodium phosphate dibasic heptahydrate (0.8 mg), and water for injection. Hydrochloric acid solution and/or sodium hydroxide solution may have been added to adjust the pH. MOUNJARO has a pH of 6.5 to 7.5.

Each single-patient-use KwikPen contains additional volume to allow for device priming.

12 CLINICAL PHARMACOLOGY

12.1 Mechanism of Action

Tirzepatide is a GIP receptor and GLP-1 receptor agonist. It contains a C20 fatty diacid that enables albumin binding and prolongs the half-life. Tirzepatide selectively binds to and activates both the GIP and GLP-1 receptors, the targets for native GIP and GLP-1.

Tirzepatide enhances first- and second-phase insulin secretion, and reduces glucagon levels, both in a glucose-dependent manner.

12.2 Pharmacodynamics

Tirzepatide lowers fasting and postprandial glucose concentration, decreases food intake, and reduces body weight in patients with type 2 diabetes mellitus.

First and Second-Phase Insulin Secretion

Tirzepatide enhances the first- and second-phase insulin secretion. (Figure 1)

Figure 1: Mean insulin concentration at 0-120 minutes during hyperglycemic clamp at baseline and Week 28

Insulin Sensitivity

Tirzepatide increases insulin sensitivity, as demonstrated in a hyperinsulinemic euglycemic clamp study after 28 weeks of treatment.

Glucagon Secretion

Tirzepatide reduces fasting and postprandial glucagon concentrations. Tirzepatide 15 mg reduced fasting glucagon concentration by 28% and glucagon AUC after a mixed meal by 43%, compared with no change for placebo after 28 weeks of treatment.

Gastric Emptying

Tirzepatide delays gastric emptying. The delay is largest after the first dose and this effect diminishes over time. Tirzepatide slows post-meal glucose absorption, reducing postprandial glucose.

12.3 Pharmacokinetics

The pharmacokinetics of tirzepatide is similar between healthy subjects and patients with type 2 diabetes mellitus. Steady-state plasma tirzepatide concentrations were achieved following 4 weeks of once weekly administration. Tirzepatide exposure increases in a dose-proportional manner.

Absorption

Following subcutaneous administration, the time to maximum plasma concentration of tirzepatide ranges from 8 to 72 hours. The mean absolute bioavailability of tirzepatide following subcutaneous administration is 80%. Similar exposure was achieved with subcutaneous administration of tirzepatide in the abdomen, thigh, or upper arm.

Distribution

The mean apparent steady-state volume of distribution of tirzepatide following subcutaneous administration in patients with type 2 diabetes mellitus is approximately 10.3 L. Tirzepatide is highly bound to plasma albumin (99%).

Elimination

The apparent population mean clearance of tirzepatide is 0.061 L/h with an elimination half-life of approximately 5 days, enabling once-weekly dosing.

Metabolism

Tirzepatide is metabolized by proteolytic cleavage of the peptide backbone, beta-oxidation of the C20 fatty diacid and amide hydrolysis.

Excretion

The primary excretion routes of tirzepatide metabolites are via urine and feces. Intact tirzepatide is not observed in urine or feces.

Specific Populations

The intrinsic factors of age, gender, race, ethnicity, or body weight do not have a clinically relevant effect on the PK of tirzepatide.

Pediatric Patients

A population pharmacokinetic analysis was conducted for tirzepatide 5 mg and 10 mg using data from 93 pediatric patients 10 years of age and older with type 2 diabetes mellitus. The tirzepatide exposure in pediatric patients was within the range observed in adult patients.

Patients with Renal Impairment

Renal impairment does not impact the pharmacokinetics of tirzepatide. The pharmacokinetics of tirzepatide after a single 5 mg dose was evaluated in patients with different degrees of renal impairment (mild, moderate, severe, ESRD) compared with subjects with normal renal function. This was also shown for patients with both type 2 diabetes mellitus and renal impairment based on data from clinical studies [see Use in Specific Populations (8.6)].

Patients with Hepatic Impairment

Hepatic impairment does not impact the pharmacokinetics of tirzepatide. The pharmacokinetics of tirzepatide after a single 5 mg dose was evaluated in patients with different degrees of hepatic impairment (mild, moderate, severe) compared with subjects with normal hepatic function [see Use in Specific Populations (8.7)].

Drug Interactions Studies

Potential for Tirzepatide to Influence the Pharmacokinetics of Other Drugs

In vitro studies have shown low potential for tirzepatide to inhibit or induce CYP enzymes, and to inhibit drug transporters.

MOUNJARO delays gastric emptying and thereby has the potential to impact the absorption of concomitantly administered oral medications [see Drug Interactions (7.2)].

The impact of tirzepatide on gastric emptying was greatest after a single dose of 5 mg and diminished after subsequent doses.

Following a first dose of tirzepatide 5 mg, acetaminophen maximum concentration (Cmax) was reduced by 50%, and the median peak plasma concentration (tmax) occurred 1 hour later. After coadministration at week 4, there was no meaningful impact on acetaminophen Cmax and tmax. Overall acetaminophen exposure (AUC0-24hr) was not influenced.

Following administration of a combined oral contraceptive (0.035 mg ethinyl estradiol and 0.25 mg norgestimate) in the presence of a single dose of tirzepatide 5 mg, mean Cmax of ethinyl estradiol, norgestimate, and norelgestromin was reduced by 59%,66%, and 55%, while mean AUC was reduced by 20%, 21%, and 23%, respectively. A delay in tmax of 2.5 to 4.5 hours was observed.

12.6 Immunogenicity

The observed incidence of anti-drug antibodies is highly dependent on the sensitivity and specificity of the assay. Differences in assay methods preclude meaningful comparisons of the incidence of anti-drug antibodies in the trials described below with the incidence of anti-drug antibodies in other trials.

During the 40- to 104-week treatment periods with ADA sampling conducted up to 44 to 108 weeks in seven clinical trials in adults with type 2 diabetes mellitus [see Clinical Studies (14)], 51% (2,570/5,025) of MOUNJARO-treated patients developed anti-tirzepatide antibodies. In these trials, anti-tirzepatide antibody formation in 34% and 14% of MOUNJARO-treated adult patients showed cross-reactivity to native GIP or native GLP-1, respectively.

Of the 2,570 MOUNJARO-treated patients who developed anti-tirzepatide antibodies during the treatment periods in these seven trials, 2% and 2% developed neutralizing antibodies against tirzepatide activity on the GIP or GLP-1 receptors, respectively, and 0.9% and 0.4% developed neutralizing antibodies against native GIP or GLP-1, respectively.

During the 30-week double-blind placebo-controlled period of the glycemic control trial in pediatric patients 10 years of age or older with type 2 diabetes mellitus [see Clinical Studies (14.5)], 30/61 (49%) of MOUNJARO-treated pediatric patients developed anti-tirzepatide antibodies. Anti-tirzepatide antibodies showed cross reactivity to native GIP or native GLP-1 in 26% and 8% of MOUNJARO-treated pediatric patients, respectively. There were no neutralizing antibodies against tirzepatide activity on the GIP or GLP-1 receptors. No pediatric patients developed neutralizing antibodies against native GIP or GLP-1.

There was no identified clinically significant effect of anti-tirzepatide antibodies on pharmacokinetics or effectiveness of MOUNJARO. More MOUNJARO-treated adult and pediatric patients who developed anti-tirzepatide antibodies experienced hypersensitivity reactions or injection site reactions than those who did not develop these antibodies [see Adverse Reactions (6.1)].

13 NONCLINICAL TOXICOLOGY

13.1 Carcinogenesis, Mutagenesis, Impairment of Fertility

A 2-year carcinogenicity study was conducted with tirzepatide in male and female rats at doses of 0.15, 0.50, and 1.5 mg/kg (0.1-, 0.4-, and 1-fold the MRHD of 15 mg once weekly based on AUC) administered by subcutaneous injection twice weekly. A statistically significant increase in thyroid C-cell adenomas was observed in males (≥0.5 mg/kg) and females (≥0.15 mg/kg), and a statistically significant increase in thyroid C-cell adenomas and carcinomas combined was observed in males and females at all doses examined. In a 6-month carcinogenicity study in rasH2 transgenic mice, tirzepatide at doses of 1, 3, and 10 mg/kg administered by subcutaneous injection twice weekly was not tumorigenic.

Tirzepatide was not genotoxic in a rat bone marrow micronucleus assay.

In fertility and early embryonic development studies, male and female rats were administered twice weekly subcutaneous doses of 0.5, 1.5, or 3 mg/kg (0.3-, 1-, and 2-fold and 0.3-, 0.9-, and 2-fold, respectively, the MRHD of 15 mg once weekly based on AUC). No effects of tirzepatide were observed on sperm morphology, mating, fertility, and conception. In female rats, an increase in the number of females with prolonged diestrus and a decrease in the mean number of corpora lutea resulting in a decrease in the mean number of implantation sites and viable embryos was observed at all dose levels. These effects were considered secondary to the pharmacological effects of tirzepatide on food consumption and body weight.

14 CLINICAL STUDIES

14.1 Overview of Clinical Studies

The effectiveness of MOUNJARO as an adjunct to diet and exercise to improve glycemic control in adults with type 2 diabetes mellitus was established in five trials. In these trials, MOUNJARO was studied as monotherapy (SURPASS-1); as an add-on to metformin, sulfonylureas, and/or sodium-glucose co-transporter 2 inhibitors (SGLT2 inhibitors) (SURPASS-2, -3, and -4); and in combination with basal insulin with or without metformin (SURPASS-5). In these trials, MOUNJARO (5 mg, 10 mg, and 15 mg given subcutaneously once weekly) was compared with placebo, semaglutide 1 mg, insulin degludec, and/or insulin glargine [see Clinical Studies (14.2, 14.3, 14.4)].

In adult patients with type 2 diabetes mellitus, treatment with MOUNJARO produced a statistically significant reduction from baseline in HbA1c compared to placebo. The effectiveness of MOUNJARO was not impacted by age, gender, race, ethnicity, region, or by baseline BMI, HbA1c, diabetes duration, or renal function.

MOUNJARO 5 mg and 10 mg was studied in pediatric patients 10 years of age and older with type 2 diabetes in combination with metformin and/or basal insulin [see Clinical Studies (14.5)].

14.2 Monotherapy Use of MOUNJARO in Adult Patients with Type 2 Diabetes Mellitus

SURPASS-1 (NCT03954834) was a 40-week double-blind trial that randomized 478 adult patients with type 2 diabetes mellitus with inadequate glycemic control with diet and exercise to subcutaneous MOUNJARO 5 mg, MOUNJARO 10 mg, MOUNJARO 15 mg, or placebo once weekly.

Patients had a mean age of 54 years, and 52% were men. The mean duration of type 2 diabetes mellitus was 4.7 years, and the mean BMI was 32 kg/m^2. Overall, 36% were White, 35% were Asian, 25% were American Indians/Alaska Natives, and 5% were Black or African American; 43% identified as Hispanic or Latino ethnicity.

Monotherapy with MOUNJARO 5 mg, 10 mg and 15 mg once weekly for 40 weeks resulted in a statistically significant reduction in HbA1c compared with placebo (see Table 4).

Table 4: Results at Week 40 in a Trial of MOUNJARO as Monotherapy in Adult Patients with Type 2 Diabetes Mellitus with Inadequate Glycemic Control with Diet and Exercise
 | Placebo | MOUNJARO 5 mg | MOUNJARO 10 mg | MOUNJARO 15 mg
Modified Intent-to-Treat (mITT) Population (N)a | 113 | 121 | 121 | 120
HbA1c (%)
Baseline (mean) | 8.1 | 8.0 | 7.9 | 7.9
Change at Week 40b | -0.1 | -1.8 | -1.7 | -1.7
Difference from placebob (95% CI) | -- | -1.7c (-2.0, -1.4) | -1.6c (-1.9, -1.3) | -1.6c (-1.9, -1.3)
Patients (%) achieving HbA1c <7%d | 23 | 82c | 85c | 78c
Fasting Serum Glucose (mg/dL)
Baseline (mean) | 155 | 154 | 153 | 154
Change at Week 40b | 4 | -40 | -40 | -39
Difference from placebob (95% CI) | -- | -43c (-55, -32) | -43c (-55, -32) | -42c (-54, -30)
Body Weight (kg)
Baseline (mean) | 84.5 | 87.0 | 86.2 | 85.5
Change at Week 40b | -1.0 | -6.3 | -7.0 | -7.8
Difference from placebob (95% CI) | -- | -5.3c (-6.8, -3.9) | -6.0c (-7.4, -4.6) | -6.8c (-8.3, -5.4)
a The modified intent-to-treat population consists of all randomly assigned participants who were exposed to at least 1 dose of study drug. Patients who discontinued study treatment because they did not meet study enrollment criteria were excluded. During the trial, rescue medication (additional antihyperglycemic medication) was initiated by 25%, 2%, 3%, and 2% of patients randomized to placebo, MOUNJARO 5 mg, 10 mg, and 15 mg, respectively. At Week 40 the HbA1c data were missing for 12%, 6%, 7%, and 14% of patients randomized to placebo, MOUNJARO 5 mg, 10 mg, and 15 mg, respectively. Missing Week 40 data were imputed using placebo-based multiple imputation.
b Least-squares mean from ANCOVA adjusted for baseline value and other stratification factors.
c p<0.001 (two-sided) for superiority versus placebo, adjusted for multiplicity.
d Analyzed using logistic regression adjusted for baseline value and other stratification factors.

14.3 MOUNJARO Use in Combination with Metformin, Sulfonylureas, and/or SGLT2 Inhibitors in Adult Patients with Type 2 Diabetes Mellitus

Add-on to metformin

SURPASS-2 (NCT03987919) was a 40-week open-label trial (double-blind with respect to MOUNJARO dose assignment) that randomized 1879 adult patients with type 2 diabetes mellitus with inadequate glycemic control on stable doses of metformin alone to the addition of subcutaneous MOUNJARO 5 mg, MOUNJARO 10 mg, or MOUNJARO 15 mg once weekly or subcutaneous semaglutide 1 mg once weekly.

Patients had a mean age of 57 years and 47% were men. The mean duration of type 2 diabetes mellitus was 8.6 years, and the mean BMI was 34 kg/m^2. Overall, 83% were White, 4% were Black or African American, and 1% were Asian; 70% identified as Hispanic or Latino ethnicity.

Treatment with MOUNJARO 10 mg and 15 mg once weekly for 40 weeks resulted in a statistically significant reduction in HbA1c compared with semaglutide 1 mg once weekly (see Table 5 and Figure 2).

Table 5: Results at Week 40 in a Trial of MOUNJARO versus Semaglutide 1 mg in Adult Patients with Type 2 Diabetes Mellitus Added to Metformin
 | Semaglutide 1 mg | MOUNJARO 5 mg | MOUNJARO 10 mg | MOUNJARO 15 mg
Modified Intent-to-Treat (mITT) Population (N)a | 468 | 470 | 469 | 469
HbA1c (%)
Baseline (mean) | 8.3 | 8.3 | 8.3 | 8.3
Change at Week 40b | -1.9 | -2.0 | -2.2 | -2.3
Difference from semaglutideb (95% CI) | -- | -0.2c (-0.3, -0.0) | -0.4d (-0.5, -0.3) | -0.5d (-0.6, -0.3)
Patients (%) achieving HbA1c <7%e | 79 | 82 | 86f | 86f
Fasting Serum Glucose (mg/dL)
Baseline (mean) | 171 | 174 | 174 | 172
Change at Week 40b | -49 | -55 | -59 | -60
Body Weight (kg)
Baseline (mean) | 93.7 | 92.5 | 94.8 | 93.8
Change at Week 40b | -5.7 | -7.6 | -9.3 | -11.2
Difference from semaglutideb (95% CI) | -- | -1.9c (-2.8, -1.0) | -3.6d (-4.5, -2.7) | -5.5d (-6.4, -4.6)
a The modified intent-to-treat population consists of all randomly assigned participants who were exposed to at least 1 dose of study drug. Patients who discontinued study treatment because they did not meet study enrollment criteria were excluded. During the trial, rescue medication (additional antihyperglycemic medication) was initiated by 3%, 2%, 1%, and 1% of patients randomized to semaglutide 1 mg, MOUNJARO 5 mg, 10 mg, and 15 mg, respectively. At Week 40 the HbA1c endpoint was missing for 5%, 4%, 5%, and 5% of patients randomized to semaglutide 1 mg, MOUNJARO 5 mg, 10 mg, and 15 mg, respectively. Missing Week 40 data were imputed using multiple imputation with retrieved dropout.
b Least-squares mean from ANCOVA adjusted for baseline value and other stratification factors.
c p<0.05 (two-sided) for superiority versus semaglutide, adjusted for multiplicity.
d p<0.001 (two-sided) for superiority versus semaglutide, adjusted for multiplicity.
e Analyzed using logistic regression adjusted for baseline value and other stratification factors.
f p<0.01 (two-sided) for superiority versus semaglutide, adjusted for multiplicity.

Figure 2: Mean HbA1c (%) Over Time - Baseline to Week 40

Number of patients
MOUNJARO 5mg | 470 |  |  |  |  |  |  |  |  | 451 | 470
MOUNJARO 10mg | 469 |  |  |  |  |  |  |  |  | 445 | 469
MOUNJARO 15mg | 469 |  |  |  |  |  |  |  |  | 447 | 469
Semaglutide 1mg | 468 |  |  |  |  |  |  |  |  | 443 | 468

Note: Displayed results are from modified Intent-to-Treat Full Analysis Set. (1) Observed mean value from Week 0 to Week 40, and (2) least-squares mean ± standard error at Week 40 multiple imputation (MI).

Add-on to metformin with or without SGLT2 inhibitor

SURPASS-3 (NCT03882970) was a 52-week open-label trial that randomized 1444 adult patients with type 2 diabetes mellitus with inadequate glycemic control on stable doses of metformin with or without SGLT2 inhibitor to the addition of subcutaneous MOUNJARO 5 mg, MOUNJARO 10 mg, MOUNJARO 15 mg once weekly, or insulin degludec 100 units/mL once daily. In this trial, 32% of patients were on SGLT2 inhibitor. Insulin degludec was initiated at 10 units once daily and adjusted weekly throughout the trial using a treat-to-target algorithm based on self-measured fasting blood glucose values. At Week 52, 26% of patients randomized to insulin degludec achieved the fasting serum glucose target of <90 mg/dL, and the mean daily insulin degludec dose was 49 U (0.5 U per kilogram).

Patients had a mean age of 57 years, and 56% were men. The mean duration of type 2 diabetes mellitus was 8.4 years, and the mean baseline BMI was 34 kg/m^2. Overall, 91% were White, 3% were Black or African American, and 5% were Asian; 29% identified as Hispanic or Latino ethnicity.

Treatment with MOUNJARO 10 mg and 15 mg once weekly for 52 weeks resulted in a statistically significant reduction in HbA1c compared with daily insulin degludec (see Table 6).

Table 6: Results at Week 52 in a Trial of MOUNJARO versus Insulin Degludec in Adult Patients with Type 2 Diabetes Mellitus Added to Metformin with or without SGLT2 Inhibitor
 | Insulin Degludec | MOUNJARO 5 mg | MOUNJARO 10 mg | MOUNJARO 15 mg
Modified Intent-to-Treat (mITT)a Population (N) | 359 | 358 | 360 | 358
HbA1c (%)
Baseline (mean) | 8.1 | 8.2 | 8.2 | 8.2
Change at Week 52b | -1.3 | -1.9 | -2.0 | -2.1
Difference from insulin degludecb (95% CI) | -- | -0.6c (-0.7, -0.5) | -0.8c (-0.9, -0.6) | -0.9c (-1.0, -0.7)
Patients (%) achieving HbA1c <7%d | 58 | 79c | 82c | 83c
Fasting Serum Glucose (mg/dL)
Baseline (mean) | 167 | 172 | 170 | 168
Change at Week 52b | -51 | -47 | -50 | -54
Body Weight (kg)
Baseline (mean) | 94.0 | 94.4 | 93.8 | 94.9
Change at Week 52b | 1.9 | -7.0 | -9.6 | -11.3
Difference from insulin degludecb (95% CI) | -- | -8.9c (-10.0, -7.8) | -11.5c (-12.6, -10.4) | -13.2c (-14.3, -12.1)
a The modified intent-to-treat population consists of all randomly assigned participants who were exposed to at least 1 dose of study drug. Patients who discontinued study treatment because they did not meet study enrollment criteria were excluded. During the trial, rescue medication (additional antihyperglycemic medication) was initiated by 1%,1%, 1%, and 2% of patients randomized to insulin degludec, MOUNJARO 5 mg, 10 mg, and 15 mg, respectively. At Week 52 the HbA1c endpoint was missing for 9%, 6%, 10%, and 5% of patients randomized to insulin degludec, MOUNJARO 5 mg, 10 mg, and 15 mg, respectively. Missing Week 52 data were imputed using multiple imputation with retrieved dropout.
b Least-squares mean from ANCOVA adjusted for baseline value and other stratification factors.
c p<0.001 (two-sided) for superiority versus insulin degludec, adjusted for multiplicity.
d Analyzed using logistic regression adjusted for baseline value and other stratification factors.

Add-on to 1-3 oral anti-hyperglycemic agents (metformin, sulfonylurea, or SGLT-2 inhibitor)

SURPASS-4 (NCT03730662) was a 104-week open-label trial (52-week primary endpoint) that randomized 2002 adult patients with type 2 diabetes mellitus with increased cardiovascular risk to subcutaneous MOUNJARO 5 mg, MOUNJARO 10 mg, MOUNJARO 15 mg once weekly, or insulin glargine 100 units/mL once daily (1:1:1:3 ratio) on a background of metformin (95%) and/or sulfonylureas (54%) and/or SGLT2 inhibitors (25%).

Patients had a mean age of 64 years, and 63% were men. The mean duration of type 2 diabetes mellitus was 11.8 years, and the mean baseline BMI was 33 kg/m^2. Overall, 82% were White, 4% were Black or African American, and 4% were Asian; 48% identified as Hispanic or Latino ethnicity. Across all treatment groups, 87% had a history of cardiovascular disease. At baseline, eGFR was ≥90 mL/min/1.73 m^2 in 43%, 60 to 90 mL/min/1.73 m^2 in 40%, 45 to 60 mL/min/1.73 m^2 in 10%, and 30 to 45 mL/min/1.73 m^2 in 6% of patients.

Insulin glargine was initiated at 10 U once daily and adjusted weekly throughout the trial using a treat-to-target algorithm based on self-measured fasting blood glucose values. At Week 52, 30% of patients randomized to insulin glargine achieved the fasting serum glucose target of <100 mg/dL, and the mean daily insulin glargine dose was 44 U (0.5 U per kilogram).

Treatment with MOUNJARO 10 mg and 15 mg once weekly for 52 weeks resulted in a statistically significant reduction in HbA1c compared with insulin glargine once daily (see Table 7).

Table 7: Results at Week 52 in a Trial of MOUNJARO versus Insulin Glargine in Adult Patients with Type 2 Diabetes Mellitus Added to Metformin and/or Sulfonylurea and/or SGLT2 Inhibitor
 | Insulin Glargine | MOUNJARO 5 mg | MOUNJARO 10 mg | MOUNJARO 15 mg
Modified Intent-to-Treat (mITT) Population (N)a | 998 | 328 | 326 | 337
HbA1c (%)
Baseline (mean) | 8.5 | 8.5 | 8.6 | 8.5
Change at Week 52b | -1.4 | -2.1 | -2.3 | -2.4
Difference from insulin glargineb (95% CI) | -- | -0.7c (-0.9, -0.6) | -0.9c (-1.1, -0.8) | -1.0c (-1.2, -0.9)
Patients (%) achieving HbA1c <7%d | 49 | 75c | 83c | 85c
Fasting Serum Glucose (mg/dL)
Baseline (mean) | 168 | 172 | 176 | 174
Change at Week 52b | -49 | -44 | -50 | -55
Body Weight (kg)
Baseline (mean) | 90.2 | 90.3 | 90.6 | 90.0
Change at Week 52b | 1.7 | -6.4 | -8.9 | -10.6
Difference from insulin glargineb (95% CI) | -- | -8.1c (-8.9, -7.3) | -10.6c (-11.4, -9.8) | -12.2c (-13.0, -11.5)
a The modified intent-to-treat population consists of all randomly assigned participants who were exposed to at least 1 dose of study drug. Patients who discontinued study treatment because they did not meet study enrollment criteria were excluded. During the trial, rescue medication (additional antihyperglycemic medication) was initiated by 1%, 0%, 0%, and 1% of patients randomized to insulin glargine, MOUNJARO 5 mg, 10 mg, and 15 mg, respectively. At Week 52 the HbA1c endpoint was missing for 9%, 9%, 6%, and 4% of patients randomized to insulin glargine, MOUNJARO 5 mg, 10 mg, and 15 mg, respectively. Missing Week 52 data were imputed using multiple imputation with retrieved dropout.
b Least-squares mean from ANCOVA adjusted for baseline value and other stratification factors.
c p<0.001 (two-sided) for superiority versus insulin glargine, adjusted for multiplicity.
d Analyzed using logistic regression adjusted for baseline value and other stratification factors.

14.4 MOUNJARO Use in Combination with Basal Insulin with or without Metformin in Adult Patients with Type 2 Diabetes Mellitus

SURPASS-5 (NCT04039503) was a 40-week double-blind trial that randomized 475 adult patients with type 2 diabetes mellitus with inadequate glycemic control on insulin glargine 100 units/mL, with or without metformin, to subcutaneous MOUNJARO 5 mg, MOUNJARO 10 mg, MOUNJARO 15 mg once weekly, or placebo. The dose of background insulin glargine was adjusted using a treat-to-target algorithm based on self-measured fasting blood glucose values, targeting <100 mg/dL.

Patients had a mean age of 61 years, and 56% were men. The mean duration of type 2 diabetes mellitus was 13.3 years, and the mean baseline BMI was 33 kg/m^2. Overall, 80% were White, 1% were Black or African American, and 18% were Asian; 5% identified as Hispanic or Latino ethnicity.

The mean dose of insulin glargine at baseline was 34, 32, 35, and 33 units/day for patients receiving MOUNJARO 5 mg, 10 mg, 15 mg, and placebo, respectively. At randomization, the initial insulin glargine dose in patients with HbA1c ≤8.0% was reduced by 20%. At week 40, mean dose of insulin glargine was 38, 36, 29, and 59 units/day for patients receiving MOUNJARO 5 mg, 10 mg, 15 mg, and placebo, respectively.

Treatment with MOUNJARO 5 mg once weekly, 10 mg once weekly and 15 mg once weekly for 40 weeks resulted in a statistically significant reduction in HbA1c compared with placebo (see Table 8).

Table 8: Results at Week 40 in a Trial of MOUNJARO Added to Basal Insulin with or without Metformin in Adult Patients with Type 2 Diabetes Mellitus
 | Placebo | MOUNJARO 5 mg | MOUNJARO 10 mg | MOUNJARO 15 mg
Modified Intent-to-Treat (mITT) Population (N)a | 119 | 116 | 118 | 118
HbA1c (%)
Baseline (mean) | 8.4 | 8.3 | 8.4 | 8.2
Change at Week 40b | -0.9 | -2.1 | -2.4 | -2.3
Difference from placebob (95% CI) | -- | -1.2c (-1.5, -1.0) | -1.5c (-1.8, -1.3) | -1.5c (-1.7, -1.2)
Patients (%) achieving HbA1c <7%d | 35 | 87c | 90c | 85c
Fasting Serum Glucose (mg/dL)
Baseline (mean) | 164 | 163 | 163 | 160
Change at Week 40b | -39 | -58 | -64 | -63
Difference from placebob (95% CI) | -- | -19c (-27, -11) | -25c (-32, -17) | -23c (-31, -16)
Body Weight (kg)
Baseline (mean) | 94.2 | 95.8 | 94.6 | 96.0
Change at Week 40b | 1.6 | -5.4 | -7.5 | -8.8
Difference from placebob (95% CI) | -- | -7.1c (-8.7, -5.4) | -9.1c (-10.7, -7.5) | -10.5c (-12.1, -8.8)
a The modified intent-to-treat population consists of all randomly assigned participants who were exposed to at least 1 dose of study drug. Patients who discontinued study treatment because they did not meet study enrollment criteria were excluded. During the trial, rescue medication (additional antihyperglycemic medication) was initiated by 4%, 1%, 0%, and 1% of patients randomized to placebo, MOUNJARO 5 mg, 10 mg, and 15 mg, respectively. At Week 40 the HbA1c endpoint was missing for 2%, 6%, 3%, and 7% of patients randomized to placebo, MOUNJARO 5 mg, 10 mg, and 15 mg, respectively. Missing Week 40 data were imputed using placebo-based multiple imputation.
b Least-squares mean from ANCOVA adjusted for baseline value and other stratification factors.
c p<0.001 (two-sided) for superiority versus placebo, adjusted for multiplicity.
d Analyzed using logistic regression adjusted for baseline value and other stratification factors.

14.5 MOUNJARO Use in Combination with Metformin or Basal Insulin, or Both in Pediatric Patients 10 Years of Age and Older with Type 2 Diabetes Mellitus

SURPASS-PEDS (NCT05260021) was a 30-week double-blind, placebo-controlled trial with a 22-week open-label extension that randomized 99 pediatric patients 10 years of age and older with type 2 diabetes mellitus with inadequate glycemic control on metformin (69%), or basal insulin (8%), or both (23%) to receive subcutaneous MOUNJARO 5 mg, MOUNJARO 10 mg, or placebo once weekly as add-on therapy.

Patients had a mean age of 15 years, and 61% were female. The mean duration of type 2 diabetes mellitus was 2.4 years, mean HbA1c was 8.0%, mean weight was 97 kg, and the mean baseline BMI was 35 kg/m^2. Overall, 58% were White, 11% were Black or African American, 6% were Asian, 20% were American Indian or Alaska Native, and 5% were other races; 66% identified as Hispanic or Latino ethnicity.

Treatment with MOUNJARO 5 mg once weekly and 10 mg once weekly for 30 weeks, both pooled and individually, resulted in a statistically significant reduction in HbA1c compared with placebo (see Table 9).

Table 9: Results at Week 30 in a Trial of MOUNJARO Added to Metformin or Basal Insulin, or Both in Pediatric Patients 10 Years of Age and Older with Type 2 Diabetes Mellitus
 | Placebo | MOUNJARO 5 mg | MOUNJARO 10 mg | MOUNJARO 5 mg/10 mg pooled
Modified Intent-to-Treat (mITT) Population (N)a | 34 | 32 | 33 | 65
HbA1c (%)
Baseline (mean) | 8.0 | 8.2 | 7.9 | 8.1
Change at Week 30b | -0.2 | -1.9 | -2.2 | -2.0
Difference from placebob (95% CI) | -- | -1.7c (-2.4, -1.0) | -2.0c (-2.7, -1.3) | -1.8c (-2.4, -1.2)
Patients (%) with HbA1c ≤6.5% at Week 30d | 28 | 68c | 81c | 75c
Fasting Serum Glucose (mg/dL)
Baseline (mean) | 156f | 148f | 152f | 150f
Change at Week 30b | -5 | -35 | -51 | -43
Difference from placebob (95% CI) | -- | -30e (-53, -8) | -46c (-68, -24) | -38c (-57, -19)
BMI (kg/m^2)
Baseline (mean) | 34.7 | 33.9 | 37.7 | 35.8
Percent Change at Week 30b | -0.5 | -6.9 | -10.8 | -8.8
Difference from placebo (%)b (95% CI) | -- | -6.4c (-9.5, -3.2) | -10.3c (-13.5, -7.1) | -8.3c (-11.0, -5.6)
a The modified intent-to-treat population consists of all randomly assigned participants who were exposed to at least 1 dose of study drug. During the trial, rescue medication (additional antihyperglycemic medication) was initiated by 6%, 0%, and 0% of patients randomized to placebo, MOUNJARO 5 mg, and 10 mg, respectively. At Week 30 the HbA1c endpoint was missing for 6%, 9%, and 18% of patients randomized to placebo, MOUNJARO 5 mg, and 10 mg, respectively. Missing Week 30 data were imputed using multiple imputation with placebo wash-out or with assumption of missing at random.
b Least-squares mean from ANCOVA adjusted for baseline value and other stratification factors.
c p<0.001 (two-sided) for superiority versus placebo, adjusted for multiplicity.
d Response in (%) is calculated by combining proportion of participants achieving target in imputed datasets using Rubin's rule.
e p<0.01 (two-sided) for superiority versus placebo, adjusted for multiplicity.
f Any missing values at baseline were imputed as missing at random.

16 HOW SUPPLIED/STORAGE AND HANDLING

16.1 How Supplied

MOUNJARO is a clear, colorless to slightly yellow solution available in cartons containing 4 pre-filled single-dose pens, 1 single-dose vial, 1 multi-dose vial, or 1 Single-Patient-Use KwikPen as follows:

Single-Dose Vial and Prefilled Pen
Strength | 4 pack Single-dose Pen NDC | 1 pack Single-dose Vial NDC
2.5 mg/0.5 mL | 0002-1506-80 | 0002-1152-01
5 mg/0.5 mL | 0002-1495-80 | 0002-1243-01
7.5 mg/0.5 mL | 0002-1484-80 | 0002-2214-01
10 mg/0.5 mL | 0002-1471-80 | 0002-2340-01
12.5 mg/0.5 mL | 0002-1460-80 | 0002-2423-01
15 mg/0.5 mL | 0002-1457-80 | 0002-3002-01

Multi-Dose Vial
Doses per Vial | Strength | 1-pack Multi-dose Vial NDC
4 doses of 2.5 mg/0.6 mL | 10 mg/2.4 mL (4.17 mg/mL) | 0002-4052-11
4 doses of 5 mg/0.6 mL | 20 mg/2.4 mL (8.33 mg/mL) | 0002-4103-11
4 doses of 7.5 mg/0.6 mL | 30 mg/2.4 mL (12.5 mg/mL) | 0002-4210-11
4 doses of 10 mg/0.6 mL | 40 mg/2.4 mL (16.7 mg/mL) | 0002-4304-11
4 doses of 12.5 mg/0.6 mL | 50 mg/2.4 mL (20.8 mg/mL) | 0002-4523-11
4 doses of 15 mg/0.6 mL | 60 mg/2.4 mL (25 mg/mL) | 0002-4612-11

Single-Patient-Use KwikPen (with four weekly doses)
Doses per KwikPen | Strength | 1-pack Single-Patient-Use KwikPen NDC
4 doses of 2.5 mg | 10 mg/2.4 mL (4.17 mg/mL) | 0002-3466-11
4 doses of 5 mg | 20 mg/2.4 mL (8.33 mg/mL) | 0002-3455-11
4 doses of 7.5 mg | 30 mg/2.4 mL (12.5 mg/mL) | 0002-3444-11
4 doses of 10 mg | 40 mg/2.4 mL (16.7 mg/mL) | 0002-3433-11
4 doses of 12.5 mg | 50 mg/2.4 mL (20.8 mg/mL) | 0002-3422-11
4 doses of 15 mg | 60 mg/2.4 mL (25 mg/mL) | 0002-3411-11

16.2 Storage and Handling

- Do not freeze MOUNJARO. Do not use MOUNJARO if frozen.
- Protect MOUNJARO from heat and light.
- Store MOUNJARO in the original carton to protect from light.

MOUNJARO Single-dose Pen and Single-dose Vial

- Store MOUNJARO single-dose pen and single-dose vial in a refrigerator at 2°C to 8°C (36°F to 46°F).
- If needed, each single-dose pen or single-dose vial can be stored unrefrigerated at temperatures not to exceed 30°C (86°F) for up to 21 days.

MOUNJARO Multi-dose Vial or Single-Patient-Use KwikPen

Unopened vial or single-patient-use KwikPen:

- Store unopened multi-dose vial or single-patient-use KwikPen in the refrigerator at 2°C to 8°C (36°F to 46°F). The unopened multi-dose vial or single-patient-use KwikPen can be used until the expiration date on the label if kept in the refrigerator.
- If stored at room temperature [up to 30°C (86°F)], throw away unopened multi-dose vial or single-patient-use KwikPen after 30 days.

After vial or single-patient-use KwikPen has been opened:

- Store opened (in-use) multi-dose vial or single-patient-use KwikPen in the original carton in the refrigerator at 2°C to 8°C (36°F to 46°F) or at room temperature [up to 30°C (86°F)].
- Throw away opened multi-dose vial or single-patient-use KwikPen after a total of 30 days at room temperature, 30 days after first use, or after taking 4 weekly doses, even if there is medicine left in it.

17 PATIENT COUNSELING INFORMATION

Advise the patient to read the FDA-approved patient labeling (Medication Guide and Instructions for Use).

Risk of Thyroid C-Cell Tumors

Inform patients that MOUNJARO causes thyroid C-cell tumors in rats and that the human relevance of this finding has not been determined. Counsel patients to report symptoms of thyroid tumors (e.g., a lump in the neck, persistent hoarseness, dysphagia, or dyspnea) to their healthcare provider [see Boxed Warning and Warnings and Precautions (5.1)].

Acute Pancreatitis

Inform patients of the potential risk for acute pancreatitis and its symptoms: severe abdominal pain that sometimes radiates to the back, and which may or may not be accompanied by nausea or vomiting. Instruct patients to discontinue MOUNJARO promptly and contact their physician if pancreatitis is suspected [see Warnings and Precautions (5.2)].

Hypoglycemia with Concomitant Use of Insulin Secretagogues or Insulin

Inform patients that the risk of hypoglycemia is increased when MOUNJARO is used with an insulin secretagogue (such as a sulfonylurea) or insulin. Educate patients on the signs and symptoms of hypoglycemia [see Warnings and Precautions (5.3)].

Hypersensitivity Reactions

Inform patients that serious hypersensitivity reactions have been reported with use of MOUNJARO. Advise patients on the symptoms of hypersensitivity reactions and instruct them to stop taking MOUNJARO and seek medical advice promptly if such symptoms occur [see Warnings and Precautions (5.4)].

Acute Kidney Injury Due to Volume Depletion

Inform patients of the potential risk of acute kidney injury due to dehydration associated with gastrointestinal adverse reactions. Advise patients to take precautions to avoid fluid depletion. Inform patients of the signs and symptoms of acute kidney injury and instruct them to promptly report any of these signs or symptoms or persistent (or extended) nausea, vomiting, and diarrhea to their healthcare provider [see Warnings and Precautions (5.5)].

Severe Gastrointestinal Adverse Reactions

Inform patients of the potential risk of severe gastrointestinal adverse reactions. Instruct patients to contact their healthcare provider if they have severe or persistent gastrointestinal symptoms [see Warnings and Precautions (5.6)].

Diabetic Retinopathy Complications in Patients with a History of Diabetic Retinopathy

Inform patients to contact their healthcare provider if changes in vision are experienced during treatment with MOUNJARO [see Warnings and Precautions (5.7)].

Acute Gallbladder Disease

Inform patients of the risk of acute gallbladder disease. Instruct patients to contact their healthcare provider for appropriate clinical follow-up if gallbladder disease is suspected [see Warnings and Precautions (5.8)].

Pulmonary Aspiration During General Anesthesia or Deep Sedation

Inform patients that MOUNJARO may cause their stomach to empty more slowly which may lead to complications with anesthesia or deep sedation during planned surgeries or procedures. Instruct patients to inform healthcare providers prior to any planned surgeries or procedures if they are taking MOUNJARO [see Warnings and Precautions (5.9)].

Never Share a MOUNJARO KwikPen Between Patients

Advise patients that they must never share a MOUNJARO KwikPen with another person, even if the pen needle is changed, because doing so carries a risk for transmission of blood-borne pathogens [see Warnings and Precautions (5.10)].

Pregnancy

Advise a pregnant woman of the potential risk to a fetus. Advise women to inform their healthcare provider if they are pregnant or intend to become pregnant [see Use in Specific Populations (8.1)].

Contraception

Use of MOUNJARO may reduce the efficacy of oral hormonal contraceptives. Advise patients using oral hormonal contraceptives to switch to a non-oral contraceptive method or add a barrier method of contraception for 4 weeks after initiation and for 4 weeks after each dose escalation with MOUNJARO [see Drug Interactions (7.2), Use in Specific Populations (8.3), and Clinical Pharmacology (12.3)].

Administration

Instruct patients how to prepare and administer the correct dose of MOUNJARO and assess their ability to inject subcutaneously to ensure the proper administration of MOUNJARO. Instruct patients using MOUNJARO vials to always use a new syringe and needle for each injection. Use a syringe appropriate for dose administration (e.g., a 1 mL syringe capable of measuring a 0.5 mL or 0.6 mL dose). Notify the patient of which MOUNJARO presentation they will be receiving and ensure training is appropriate for the specific MOUNJARO presentation. Advise patients to refer to the IFU in case of any change in the presentation. Advise caregivers that MOUNJARO KwikPen is not recommended for self-administration by pediatric patients or those with visual impairment unless their healthcare provider determines the patient can properly administer. [see Dosage and Administration (2.2)].

Missed Doses

Inform patients if a dose is missed, it should be administered as soon as possible within 4 days after the missed dose. If more than 4 days have passed, the missed dose should be skipped and the next dose should be administered on the regularly scheduled day. In each case, inform patients to resume their regular once weekly dosing schedule [see Dosage and Administration (2.1)].

Marketed by: Lilly USA, LLC, Indianapolis, IN 46285, USA
Copyright © 2022, 2026, Eli Lilly and Company. All rights reserved.

Pat.: www.lilly.com/patents

MOU-0010-USPI-20260120

Mounjaro Medication Guide

Medication Guide
MOUNJARO® [mown-JAHR-OH]
(tirzepatide)
injection, for subcutaneous use

Do not share your MOUNJARO KwikPen or needles with other people, even if the needle has been changed. You may give other people a serious infection, or get a serious infection from them.

What is the most important information I should know about MOUNJARO?
MOUNJARO may cause serious side effects, including:

- Possible thyroid tumors, including cancer. Tell your healthcare provider if you get a lump or swelling in your neck, hoarseness, trouble swallowing, or shortness of breath. These may be symptoms of thyroid cancer. In studies with rats, MOUNJARO and medicines that work like MOUNJARO caused thyroid tumors, including thyroid cancer. It is not known if MOUNJARO will cause thyroid tumors, or a type of thyroid cancer called medullary thyroid carcinoma (MTC) in people.
- Do not use MOUNJARO if you or any of your family have ever had a type of thyroid cancer called medullary thyroid carcinoma (MTC), or if you have an endocrine system condition called Multiple Endocrine Neoplasia syndrome type 2 (MEN 2).

What is MOUNJARO?

- MOUNJARO is an injectable prescription medicine that is used along with diet and exercise to improve blood sugar (glucose) in adults and children 10 years of age and older with type 2 diabetes mellitus.
- It is not known if MOUNJARO is safe and effective for use in children under 10 years of age.

Do not use MOUNJARO if:

- you or any of your family have ever had a type of thyroid cancer called MTC or if you have an endocrine system condition called MEN 2.
- you have had a serious allergic reaction to tirzepatide or any of the ingredients in MOUNJARO. See the end of this Medication Guide for a complete list of ingredients in MOUNJARO. See "What are the possible side effects of MOUNJARO?" for symptoms of a serious allergic reaction.

Before using MOUNJARO, tell your healthcare provider about all of your medical conditions, including if you:

- have or have had problems with your pancreas.
- have severe problems with your stomach, such as slowed emptying of your stomach (gastroparesis) or problems with digesting food.
- have a history of diabetic retinopathy.
- are scheduled to have surgery or other procedures that use anesthesia or deep sleepiness (deep sedation).
- are pregnant or plan to become pregnant. It is not known if MOUNJARO will harm your unborn baby. Tell your healthcare provider if you become pregnant while using MOUNJARO.
  - Birth control pills by mouth may not work as well while using MOUNJARO. If you take birth control pills by mouth, your healthcare provider may recommend another type of birth control for 4 weeks after you start MOUNJARO and for 4 weeks after each increase in your dose of MOUNJARO. Talk to your healthcare provider about birth control methods that may be right for you while using MOUNJARO.
- are breastfeeding or plan to breastfeed. MOUNJARO may pass into your breast milk. Talk to your healthcare provider about the best way to feed your baby while using MOUNJARO.

Tell your healthcare provider about all the medicines you take, including prescription and over-the-counter medicines, vitamins, and herbal supplements. MOUNJARO may affect the way some medicines work, and some medicines may affect the way MOUNJARO works.
Before using MOUNJARO, talk to your healthcare provider about low blood sugar and how to manage it. Tell your healthcare provider if you are taking other medicines to treat diabetes including insulin or sulfonylureas.
Know the medicines you take. Keep a list of them to show your healthcare provider and pharmacist when you get a new medicine.

How should I use MOUNJARO?

- Read the Instructions for Use that comes with MOUNJARO.
- Use MOUNJARO exactly as your healthcare provider tells you to.
- Your healthcare provider should show you how to prepare and inject your dose of MOUNJARO before injecting for the first time.
- A caregiver may give you MOUNJARO injections or you may self-inject if a healthcare provider determines that it is appropriate.
- Children should not inject themselves with MOUNJARO KwikPen. An adult caregiver should give a child his or her injections with MOUNJARO KwikPen.
- Self-injection is not recommended for people who are visually impaired.
- If using MOUNJARO vials, always use a new syringe and needle for each injection.
- Inject MOUNJARO under the skin (subcutaneously) of your stomach (abdomen), thigh, or another person should inject in the back of the upper arm. Do not inject MOUNJARO into a muscle (intramuscularly) or vein (intravenously).
- Use MOUNJARO 1 time each week, at any time of the day.
- You may change the day of the week you use MOUNJARO as long as the time between the 2 doses is at least 3 days (72 hours).
- If you miss a dose of MOUNJARO, take the missed dose as soon as possible within 4 days (96 hours) after the missed dose. If more than 4 days have passed, skip the missed dose and take your next dose on the regularly scheduled day. Do not take 2 doses of MOUNJARO within 3 days of each other.
- MOUNJARO may be taken with or without food.
- Do not mix insulin and MOUNJARO together in the same injection.
- You may give an injection of MOUNJARO and insulin in the same body area (such as your stomach area), but not right next to each other.
- Change (rotate) your injection site with each weekly injection. Do not use the same site for each injection.
- If you take too much MOUNJARO, call your healthcare provider or Poison Help line at 1-800-222-1222 or go to the nearest hospital emergency room right away.

What are the possible side effects of MOUNJARO?
MOUNJARO may cause serious side effects, including:

- See “What is the most important information I should know about MOUNJARO?”
- inflammation of your pancreas (pancreatitis). Stop using MOUNJARO and call your healthcare provider right away if you have severe pain in your stomach area (abdomen) that will not go away, with or without nausea or vomiting. Sometimes you may feel the pain from your abdomen to your back.
- low blood sugar (hypoglycemia). Your risk for getting low blood sugar may be higher if you use MOUNJARO with another medicine that can cause low blood sugar, such as a sulfonylurea or insulin.
  Signs and symptoms of low blood sugar may include:

- dizziness or light-headedness
- sweating
- confusion or drowsiness
- headache

- blurred vision
- slurred speech
- shakiness
- fast heartbeat

- anxiety, irritability, or mood changes
- hunger
- weakness
- feeling jittery

- serious allergic reactions. Stop using MOUNJARO and get medical help right away if you have any symptoms of a serious allergic reaction including:

- swelling of your face, lips, tongue, or throat
- problems breathing or swallowing
- severe rash or itching

- fainting or feeling dizzy
- very rapid heartbeat

- dehydration leading to kidney problems. Diarrhea, nausea, and vomiting may cause a loss of fluids (dehydration) which may cause kidney problems. It is important for you to drink fluids to help reduce your chance of dehydration. Tell your healthcare provider right away if you have nausea, vomiting, or diarrhea that does not go away.
- severe stomach problems. Stomach problems, sometimes severe, have been reported in people who use MOUNJARO. Tell your healthcare provider if you have stomach problems that are severe or will not go away.
- changes in vision. Tell your healthcare provider if you have changes in vision during treatment with MOUNJARO.
- gallbladder problems. Gallbladder problems have happened in some people who use MOUNJARO. Tell your healthcare provider right away if you get symptoms of gallbladder problems which may include:

- pain in your upper stomach (abdomen)
- fever

- yellowing of skin or eyes (jaundice)
- clay-colored stools

- food or liquid getting into the lungs during surgery or other procedures that use anesthesia or deep sleepiness (deep sedation). MOUNJARO may increase the chance of food getting into your lungs during surgery or other procedures. Tell all your healthcare providers that you are taking MOUNJARO before you are scheduled to have surgery or other procedures.

The most common side effects of MOUNJARO include:

- nausea
- diarrhea
- decreased appetite
- vomiting

- constipation
- indigestion
- stomach (abdominal) pain

Talk to your healthcare provider if you have any side effect that bothers you or that does not go away. These are not all the possible side effects of MOUNJARO. Call your doctor for medical advice about side effects. You may report side effects to FDA at 1-800-FDA-1088.

How should I store MOUNJARO?

- Store MOUNJARO in the original carton to protect it from light.
- Do not freeze MOUNJARO. Do not use MOUNJARO if frozen.
- Store each single-dose pen or single-dose vial in the refrigerator between 36⁰F to 46⁰F (2⁰C to 8⁰C). If needed, each single-dose pen or single-dose vial can be stored at room temperature up to 86⁰F (30⁰C) for up to 21 days.
- Store multi-dose vial or single-patient-use KwikPen in the refrigerator between 36°F to 46°F (2°C to 8°C) or at room temperature [up to 86°F (30°C)]. Throw away the multi-dose vial or single-patient-use KwikPen after a total of 30 days at room temperature, 30 days after first use, or after taking 4 weekly doses, even if it still has medicine in it.

Keep MOUNJARO and all medicines out of the reach of children.

General information about the safe and effective use of MOUNJARO.
Medicines are sometimes prescribed for purposes other than those listed in a Medication Guide. Do not use MOUNJARO for a condition for which it was not prescribed. Do not give MOUNJARO to other people, even if they have the same symptoms you have. It may harm them. You can ask your pharmacist or healthcare provider for information about MOUNJARO that is written for health professionals.

What are the ingredients in MOUNJARO?
Active ingredient: tirzepatide
Inactive ingredients: sodium chloride, sodium phosphate dibasic heptahydrate, and water for injection. Benzyl alcohol, glycerin, and phenol are also inactive ingredients in the multi-dose vial and single-patient-use KwikPen. Hydrochloric acid solution and/or sodium hydroxide solution may have been added to adjust the pH.
MOUNJARO® and KwikPen® are registered trademarks of Eli Lilly and Company.
Marketed by: Lilly USA, LLC Indianapolis, IN 46285, USA
Copyright © 2022, 2026, Eli Lilly and Company. All rights reserved.
For more information, go to www.MOUNJARO.com or call 1-800-545-5979.

This Medication Guide has been approved by the U.S. Food and Drug Administration

Revised: January 2026

MOU-0008-MG-20260120

Mounjaro Single-Dose Pen Instructions for Use

INSTRUCTIONS FOR USE
MOUNJARO® (mown-JAHR-OH)
(tirzepatide)
injection, for subcutaneous use
2.5 mg/0.5 mL single-dose pen
5 mg/0.5 mL single-dose pen
7.5 mg/0.5 mL single-dose pen
10 mg/0.5 mL single-dose pen
12.5 mg/0.5 mL single-dose pen
15 mg/0.5 mL single-dose pen
use 1 time each week

Important information you need to know before injecting MOUNJARO

Read this Instructions for Use and the Medication Guide before using your MOUNJARO Pen and each time you get a refill. There may be new information. This information does not take the place of talking to your healthcare provider about your medical condition or treatment.

Talk to your healthcare provider about how to inject MOUNJARO the right way.

- MOUNJARO is a single-dose prefilled pen.
- MOUNJARO is used 1 time each week.
- Inject under the skin (subcutaneously) only.
- You or another person can inject into your stomach (abdomen) or thigh.
- Another person can inject into the back of your upper arm.

Guide to parts

Preparing to inject MOUNJARO

Remove the Pen from the refrigerator.
Leave the gray base cap on until you are ready to inject.

Check the Pen label to make sure you have the right medicine and dose, and that it has not expired.
Inspect the Pen to make sure that it is not damaged.

Make sure the medicine:

- is not frozen
- is not cloudy

- is colorless to slightly yellow
- does not have particles

Wash your hands.

Step
1

Choose your injection site

Your healthcare provider can help you choose the injection site that is best for you.
You or another person can inject the medicine in your stomach (abdomen) or thigh.

Another person should give you the injection in the back of your upper arm.
Change (rotate) your injection site each week.
You may use the same area of your body but be sure to choose a different injection site in that area.

Step
2

Pull off the gray base cap

Make sure the Pen is locked.
Do not unlock the Pen until you place the clear base on your skin and are ready to inject.

Pull the gray base cap straight off and throw it away in your household trash.
Do not put the gray base cap back on – this could damage the needle.
Do not touch the needle.

Step
3

Place clear base on skin, then unlock

Place the clear base flat against your skin at the injection site.

Unlock by turning the lock ring.

Step
4

Press and hold up to 10 seconds

Press and hold the purple injection button for up to 10 seconds.
Listen for:
• First click = injection started
• Second click = injection completed

You will know your injection is complete when the gray plunger is visible.

After your injection, place the used Pen in a sharps container.

See Disposing of your used Pen.

Disposing of your used Pen

- Put your used Pen in an FDA-cleared sharps disposal container right away after use. Do not throw away (dispose of) Pens in your household trash.
- If you do not have an FDA-cleared sharps disposal container, you may use a household container that is:
  - made of a heavy-duty plastic,
  - can be closed with a tight-fitting, puncture-resistant lid, without sharps being able to come out,
  - upright and stable during use,
  - leak-resistant, and
  - properly labeled to warn of hazardous waste inside the container.
- When your sharps disposal container is almost full, you will need to follow your community guidelines for the right way to dispose of your sharps disposal container. There may be state or local laws about how you should throw away used needles and syringes. For more information about safe sharps disposal, and for specific information about sharps disposal in the state that you live in, go to the FDA's website at: http://www.fda.gov/safesharpsdisposal.
- Do not recycle your used sharps disposal container.

Storage and handling

- Store your Pen in the refrigerator between 36°F to 46°F (2°C to 8°C).
- You may store your Pen at room temperature up to 86°F (30°C) for up to 21 days.
- Do not freeze your Pen. If the Pen has been frozen, throw the Pen away and use a new Pen.
- Store your Pen in the original carton to protect your Pen from light.
- The Pen has glass parts. Handle it carefully. If you drop the Pen on a hard surface, do not use it. Use a new Pen for your injection.
- Keep your MOUNJARO Pen and all medicines out of the reach of children.

Commonly asked questions

What if I see air bubbles in my Pen?

Air bubbles are normal.

What if my Pen is not at room temperature?

It is not necessary to warm the Pen to room temperature.

What if I unlock the Pen and press the purple injection button before pulling off the gray base cap?

Do not remove the gray base cap. Throw away the Pen and get a new Pen.

What if there is a drop of liquid on the tip of the needle when I remove the gray base cap?

A drop of liquid on the tip of the needle is normal. Do not touch the needle.

Do I need to hold the injection button down until the injection is complete?

This is not necessary, but it may help you keep the Pen steady against your skin.

I heard more than 2 clicks during my injection—2 loud clicks and 1 soft one. Did I get my complete injection?

Some people may hear a soft click right before the second loud click. That is the normal operation of the Pen. Do not remove the Pen from your skin until you hear the second loud click.

I am not sure if my Pen worked the right way.

Check to see if you have received your dose. Your dose was delivered the right way if the gray plunger is visible. Also, see Step 4 of the instructions.
If you do not see the gray plunger, contact Lilly at 1-800-Lilly-Rx (1-800-545-5979) for further instructions. Until then, store your Pen safely to avoid an accidental needle stick.

What if there is a drop of liquid or blood on my skin after my injection?

This is normal. Press a cotton ball or gauze over the injection site. Do not rub the injection site.

Other information

• If you have vision problems, do not use your Pen without help from a person trained to use the MOUNJARO Pen.

Where to learn more

• If you have questions or problems with your MOUNJARO Pen, contact Lilly at 1-800-Lilly-Rx (1-800-545-5979) or call your healthcare provider.

• For more information about the MOUNJARO Pen, visit our website at www.mounjaro.com.

Scan this code to launch
www.mounjaro.com

Marketed by:

Lilly USA, LLC

Indianapolis, IN 46285, USA

MOUNJARO is a registered trademark of Eli Lilly and Company.

Copyright © 2022, 2024, Eli Lilly and Company. All rights reserved.

This Instructions for Use has been approved by the U.S. Food and Drug Administration. Revised: May 2024

MOU-0003-IFU-20240516

Mounjaro Single-Dose Vial Instructions for Use

INSTRUCTIONS FOR USE
MOUNJARO® [mown-JAHR-OH]
(tirzepatide)
injection, for subcutaneous use
2.5 mg/0.5 mL single-dose vial
5 mg/0.5 mL single-dose vial
7.5 mg/0.5 mL single-dose vial
10 mg/0.5 mL single-dose vial
12.5 mg/0.5 mL single-dose vial
15 mg/0.5 mL single-dose vial

Important information you need to know before injecting MOUNJARO

Read this Instructions for Use before you start taking MOUNJARO and each time you get a new vial. There may be new information. This information does not take the place of talking to your healthcare provider about your medical condition or your treatment.

Do not share your needles or syringes with other people. You may give other people a serious infection or get a serious infection from them.

Talk to your healthcare provider about how to inject MOUNJARO the right way.

- MOUNJARO is a single-dose vial.
- MOUNJARO is used 1 time each week.
- Inject under the skin (subcutaneously) only.
- You or another person may inject into your stomach (abdomen) or thigh.
- Another person can inject into the back of your upper arm.

Gather supplies needed to give your injection

- 1 single-dose MOUNJARO vial
- 1 syringe and 1 needle, supplied separately (for example, use a 1 mL syringe and needle as recommended by your healthcare provider)
- 1 alcohol swab
- gauze
- 1 sharps container for throwing away used needles and syringes. See “Disposing of used needles and syringes” at the end of these instructions.

Guide to parts
Vial

Needle and Syringe (not included)

Note: The needle and syringe are not included. The needle and syringe recommended by your healthcare provider may look different than the needle and syringe in this Instructions for Use.

Preparing to inject MOUNJARO

Remove the vial from the refrigerator.

Check the vial label to make sure you have the right medicine and dose, and that it has not expired.

Make sure the medicine:

- is not frozen
- is not cloudy

- is colorless to slightly yellow
- does not have particles

Always use a new syringe and needle for each injection to prevent infections and blocked needles. Do not reuse or share your syringes or needles with other people. You may give other people a serious infection or get a serious infection from them.

Wash your hands with soap and water.

Step 1:
Pull off the plastic protective cap. Do not remove the rubber stopper.

Step 2:
Wipe the rubber stopper with an alcohol swab.

Step 3:
Remove the outer wrapping from the syringe.

Step 4:
Remove the outer wrapping from the needle.
The syringe that your healthcare provider recommended may have a pre-attached needle. If the needle is attached, skip to step 6.

Step 5:
Place the needle on top of the syringe and turn until it is tight and firmly attached.

Step 6:
Remove the needle shield by pulling straight off.

Step 7:
Hold the syringe in one hand with the needle pointing up. With the other hand pull down on the plunger until the plunger tip reaches the line on the syringe indicating that 0.5 mL of air has been drawn into the syringe.

Step 8:
Push the needle through the rubber stopper of the vial.

Step 9:
Push the plunger all the way in. This puts air into the vial and makes it easier to pull the solution from the vial.

Step 10:
Turn the vial and syringe upside down. Make sure that the tip of the needle is in the liquid and slowly pull the plunger down until the plunger tip is past the 0.5 mL line.
If there are air bubbles, tap the syringe gently a few times to let any air bubbles rise to the top.

Step 11:
Slowly push the plunger up until the plunger tip reaches the 0.5 mL line.

Step 12:
Pull the syringe out of the rubber stopper of the vial.

Injecting MOUNJARO

- Inject exactly as your healthcare provider has shown you. Your healthcare provider should tell you if you should pinch the skin before injecting.
- Change (rotate) your injection site within the area you choose for each dose to reduce your risk of getting lipodystrophy (pits in skin or thickened skin) and localized cutaneous amyloidosis (skin with lumps) at the injection sites.
- Do not inject where the skin has pits, is thickened, or has lumps.
- Do not inject where the skin is tender, bruised, scaly or hard, or into scars or damaged skin.
- Do not mix MOUNJARO with any other medicine.
- Do not inject MOUNJARO in the same injection site used for other medicines.

Step 13:
Choose your injection site.
You can inject MOUNJARO under the skin (subcutaneously) of your stomach area (abdomen) or thighs.
Someone else can inject in your stomach area, thighs, or the back of the upper arms.

Step 14:
Insert the needle into your skin.

Step 15:
Push down on the plunger to inject your dose.
The needle should stay in your skin for at least 5 seconds to make sure you have injected all of your dose.

Step 16:
Pull the needle out of your skin.

- If you see blood after you take the needle out of your skin, press the injection site with a piece of gauze or an alcohol swab. Do not rub the area.
- Do not recap the needle. Recapping the needle can lead to a needle stick injury.

Disposing of used needles and syringes

- Put your used needle and syringe in an FDA-cleared sharps disposal container right away after use. Do not throw away (dispose of) loose needles and syringes in your household trash.
- If you do not have an FDA-cleared sharps disposal container, you may use a household container that is:
  - made of a heavy-duty plastic,
  - can be closed with a tight-fitting, puncture-resistant lid, without sharps being able to come out,
  - upright and stable during use,
  - leak-resistant, and
  - properly labeled to warn of hazardous waste inside the container.
- When your sharps disposal container is almost full, you will need to follow your community guidelines for the right way to dispose of your sharps disposal container. There may be state or local laws about how you should throw away used needles and syringes. For more information about safe sharps disposal, and for specific information about sharps disposal in the state that you live in, go to the FDA’s website at:
  http://www.fda.gov/safesharpsdisposal.
- Do not dispose of your used sharps disposal container in your household trash unless your community guidelines permit this. Do not recycle your used sharps disposal container.

Storing MOUNJARO

- Store all unopened vials in the refrigerator at 36°F to 46°F (2°C to 8°C).
- You may store the unopened vial at room temperature up to 86°F (30°C) for up to 21 days.
- Do not freeze. Do not use if MOUNJARO has been frozen.
- Store the vial in the original carton to protect from light.
- Throw away all opened vials after use, even if there is medicine left in the vial.

Keep MOUNJARO vials, syringes, needles, and all medicines out of the reach of children.

If you have any questions or problems with your MOUNJARO, contact Lilly at 1-800-Lilly-Rx (1-800-545-5979) or call your healthcare provider for help.

Marketed by:
Lilly USA, LLC
Indianapolis, IN 46285, USA

MOUNJARO is a registered trademark of Eli Lilly and Company.

Copyright © 2023, 2024, Eli Lilly and Company. All rights reserved.

MON-VL-0002-IFU-20240229

This Instructions for Use has been approved by the U.S. Food and Drug Administration.

Revised: February 2024

Mounjaro Multiple-Dose Vial Instructions for Use

INSTRUCTIONS FOR USE

MOUNJARO® [mown-JAHR-OH]

(tirzepatide)

injection, for subcutaneous use

Multi-dose vial

Each vial contains 4 doses, one dose taken weekly.

Important information you need to know before injecting MOUNJARO

Read this Instructions for Use before you start taking MOUNJARO and each time you get a new vial. There may be new information. This information does not take the place of talking to your healthcare provider about your medical condition or your treatment.

Do not share your needles or syringes with other people.

Talk to your healthcare provider about how to inject MOUNJARO the right way.

- MOUNJARO is a multi-dose vial. The vial contains 4 doses, one dose taken weekly.
- Inject 0.6 mL in a single weekly injection, under the skin (subcutaneously).
- You or another person may inject into your stomach (abdomen) or thigh.
- Another person can inject into the back of your upper arm.

Gather supplies needed to give your injection

- 1 multi-dose MOUNJARO vial
- 1 syringe and 1 needle, supplied separately (for example, use a 1 mL syringe and needle as recommended by your healthcare provider)
- 1 alcohol swab
- gauze
- 1 sharps container for throwing away used needles and syringes. See “Disposing of used needles and syringes” at the end of these instructions.

Guide to parts

Vial

Needle and Syringe (not included)

Note: The needle and syringe are not included. The needle and syringe recommended by your healthcare provider may look different than the needle and syringe in this Instructions for Use.

Preparing to inject MOUNJARO

Check the vial label to make sure you have the right medicine and dose, and that it has not expired.

Make sure the medicine:

- is not frozen
- is colorless to slightly yellow
- is not cloudy
- does not have particles

Always use a new syringe and needle for each injection to prevent infections and blocked needles. Do not reuse or share your syringes or needles with other people. You may give other people a serious infection or get a serious infection from them.

Wash your hands with soap and water.

Step 1:
If you are using a new vial, pull off the plastic protective cap. Do not remove the rubber stopper.

Step 2:
Wipe the rubber stopper with an alcohol swab.

Step 3:
Remove the outer wrapping from the syringe.

Step 4:
Remove the outer wrapping from the needle.
The syringe that your healthcare provider recommended may have a pre-attached needle. If the needle is attached, skip to step 6.

Step 5:
Place the needle on top of the syringe and turn until it is tight and firmly attached.

Step 6:
Remove the needle shield by pulling straight off.

Step 7:
Hold the syringe in one hand with the needle pointing up. With the other hand pull down on the plunger until the plunger tip reaches the line on the syringe indicating that 0.6 mL of air has been drawn into the syringe.

Step 8:
Push the needle through the rubber stopper of the vial.

Step 9:
Push the plunger all the way in. This puts air into the vial and makes it easier to pull the solution from the vial.

Step 10:
Turn the vial and syringe upside down. Make sure that the tip of the needle is in the liquid and slowly pull the plunger down until the plunger tip is past the 0.6 mL line.
If there are air bubbles, tap the syringe gently a few times to let any air bubbles rise to the top.

Step 11:
Slowly push the plunger up until the plunger tip reaches the 0.6 mL line.

Step 12:
Pull the syringe out of the rubber stopper of the vial.

Injecting MOUNJARO

- Inject exactly as your healthcare provider has shown you. Your healthcare provider should tell you if you should pinch the skin before injecting.
- Change (rotate) your injection site within the area you choose for each dose to reduce your risk of getting lipodystrophy (pits in skin or thickened skin) and localized cutaneous amyloidosis (skin with lumps) at the injection sites.
- Do not inject where the skin has pits, is thickened, or has lumps.
- Do not inject where the skin is tender, bruised, scaly or hard, or into scars or damaged skin.
- Do not mix MOUNJARO with any other medicine.
- Do not inject MOUNJARO in the same injection site used for other medicines.

Step 13:
Choose your injection site.
You can inject MOUNJARO under the skin (subcutaneously) of your stomach area (abdomen) or thighs.
Someone else can inject in your stomach area, thighs, or the back of the upper arms.

Step 14:
Insert the needle into your skin.

Step 15:
Push down on the plunger to inject your dose.
The needle should stay in your skin for at least 5 seconds to make sure you have injected all of your dose.

Step 16:
Pull the needle out of your skin.

- If you see blood after you take the needle out of your skin, press the injection site with a piece of gauze. Do not rub the area.
- Do not recap the needle. Recapping the needle can lead to a needle stick injury.

Disposing of used needles and syringes

- Put your used needle and syringe in an FDA-cleared sharps disposal container right away after use. Do not throw away (dispose of) loose needles and syringes in your household trash.
- If you do not have an FDA-cleared sharps disposal container, you may use a household container that is:
  - made of a heavy-duty plastic,
  - can be closed with a tight-fitting, puncture-resistant lid, without sharps being able to come out,
  - upright and stable during use,
  - leak-resistant, and
  - properly labeled to warn of hazardous waste inside the container.
- When your sharps disposal container is almost full, you will need to follow your community guidelines for the right way to dispose of your sharps disposal container. There may be state or local laws about how you should throw away used needles and syringes. For more information about safe sharps disposal, and for specific information about sharps disposal in the state that you live in, go to the FDA's website at:
  http://www.fda.gov/safesharpsdisposal.
- Do not dispose of your used sharps disposal container in your household trash unless your community guidelines permit this. Do not recycle your used sharps disposal container.

Storing MOUNJARO

- Do not freeze. Do not use if MOUNJARO has been frozen.
- Store MOUNJARO in the original carton. Keep away from light.

Unopened vial:

- Store unopened vial in the refrigerator at 36°F to 46°F (2°C to 8°C). It can be used until the expiration date on the label if kept in the refrigerator.
- If stored at room temperature [up to 86°F (30°C)], throw away unopened vial after 30 days.

After vial has been opened:

- Store opened (in-use) vial in the original carton in the refrigerator at 36°F to 46°F (2°C to 8°C) or at room temperature [up to 86°F (30°C)]. Throw away opened vial after a total of 30 days at room temperature, 30 days after first use, or after taking 4 weekly doses, even if there is medicine left in it.

Keep MOUNJARO vials, syringes, needles, and all medicines out of the reach of children.

If you have any questions or problems with your MOUNJARO, contact Lilly at 1-800-Lilly-Rx (1-800-545-5979) or call your healthcare provider for help.

Marketed by:
Lilly USA, LLC
Indianapolis, IN 46285, USA

MOUNJARO is a registered trademark of Eli Lilly and Company.

Copyright © 2026, Eli Lilly and Company. All rights reserved.
MON-MDV-0001-IFU-20260107

This Instructions for Use has been approved by the U.S. Food and Drug Administration.

Revised: January 2026

Mounjaro KwikPen Multi-Dose Pen Instructions for Use

INSTRUCTIONS FOR USE

MOUNJARO® [mown-JAHR-OH] KwikPen ® [KWIHK pehn]

(tirzepatide)

injection, for subcutaneous use

multi-dose single-patient-use prefilled pen

Each pen contains 4 fixed doses, one dose taken weekly.

This Instructions for Use contains information on how to inject MOUNJARO.

Important information you need to know before injecting MOUNJARO

Read this INSTRUCTIONS FOR USE before you start injecting MOUNJARO KwikPen (Pen) and each time you get another new Pen. There may be new information. This information does not take the place of talking to your healthcare provider about your medical condition or your treatment.

- MOUNJARO KwikPen is a disposable multi-dose single-patient-use prefilled pen. The Pen contains 4 fixed doses, one dose taken weekly. Inject a single weekly injection, under the skin (subcutaneously).
- For your weekly dose, you need to turn the dose knob all the way until it stops AND the icon is in dose window.
- After 4 doses, throw away (discard) the Pen, including the unused medicine. The Pen will prevent you from dialing a full dose after you have given yourself 4 weekly doses. Do not inject the leftover medicine. Do not transfer MOUNJARO from your Pen into a syringe.
- Do not share your MOUNJARO Pen with other people, even if the pen needle has been changed. You may give other people a serious infection or get a serious infection from them.
- People who are blind or have vision problems should not use the Pen without help from a person trained to use the Pen.

Guide to parts

Parts of the MOUNJARO Pen

Supplies needed to give your injection

- MOUNJARO KwikPen
- KwikPen-compatible Pen Needle (not included)

- Alcohol swab
- Gauze or cotton ball
- FDA-cleared sharps disposal container or household container

Preparing to inject MOUNJARO

Step 1:

- Wash your hands with soap and water.

Step 2:

- Pull the Pen cap straight off.
- Inspect the Pen and label. Do not use if:
  - the medicine name or dose strength does not match your prescription.
  - the Pen is expired (EXP) or looks damaged.
  - the medicine has been frozen, has particles, is cloudy, or is discolored. MOUNJARO should be colorless to slightly yellow.

Step 3:

- Wipe the red inner seal with an alcohol swab.

Step 4:

- Select a new pen needle. Always use a new pen needle for each injection to help prevent infections and blocked needles.
- Pull off the paper tab from the outer needle shield.

Step 5:

- Push the capped pen needle straight onto the Pen and twist the pen needle on until it is tight.

Step 6:

1. Pull off the outer needle shield and keep it. This will be reused.
2. Pull off the inner needle shield. Put it in your household trash.

a. Outer needle shield

b. Inner needle shield

Priming your Pen

Prime before each weekly injection. Priming removes air from the cartridge and makes sure that your Pen is working correctly.

Step 7:

- Slowly turn the dose knob until you hear 2 clicks and the extended line is shown in the dose window.
  This is the prime position. It can be corrected by turning the dose knob in either direction until the prime position lines up to the dose indicator.

Step 8:

- Hold your Pen with the needle pointing up.
- Tap the cartridge holder gently to collect air bubbles at the top.

Step 9:

- Release some medicine into the air by pushing the dose knob in until it stops, then slowly count to 5 while holding the dose knob. The icon must be shown in the dose window. Do not inject into your body.
  Your Pen has been primed if a small amount (a drop) of medicine comes out of the tip of the pen needle.
  - If you do not see medicine, repeat steps 7-9, no more than 2 additional times.
  - If you still do not see medicine, then change the pen needle and repeat steps 7-9, no more than 1 additional time.
  - If you still do not see medicine, contact Lilly at
    1-800-LillyRx (1-800-545-5979).

Injecting MOUNJARO

Step 10:

- Choose an injection site.
  1. You or another person can inject the medicine in your thigh or stomach (abdomen) at least 2 inches from the belly button.
  2. Another person should give you the injection in the back of your upper arm.
- Change (rotate) your injection site each week. You may use the same area of your body but be sure to choose a different injection site in that area.

a. Front b. Back

Step 11:

- Turn the dose knob all the way until it stops AND the icon is in the dose window. This is your weekly dose.
  Do not count clicks as you select the dose.

Step 12:

1. Insert the needle into your skin.
2. Inject the medicine by pushing the dose knob in until it stops then slowly count to 5 while holding the dose knob. You may notice the plunger moving with each injection. The icon must be shown in the dose window before removing the needle.

Step 13:

- Pull the needle out of your skin. A drop of medicine on the needle tip is normal. It will not affect your dose.
- Confirm the icon is in the dose window.
  If you see the icon in the dose window, you have received the full dose.
  If you do not see the icon in the dose window, insert the needle back into your skin and finish your injection. Do not redial the dose.
  If you still do not think you received the full dose, do not start over or repeat the injection. See “Troubleshooting” section for more information.

After your MOUNJARO injection

Step 14:

- If you see blood after you pull the needle out of your skin, lightly press the injection site with gauze or a cotton ball.
  Do not rub the injection site.

Step 15:

- Carefully replace the outer needle shield.

Step 16:

- Unscrew the capped needle and put the needle in a sharps container (see "Disposing of MOUNJARO KwikPen and pen needles" section).
  Do not store the Pen with the needle attached to prevent leaking, blocking the needle, and air from entering the Pen.

Step 17:

- Replace the Pen cap.
  Do not store the Pen without the Pen cap attached.

Storing your MOUNJARO KwikPen

Unused Pens:

- Store unused Pens in the refrigerator between 36°F to 46°F (2°C to 8°C).
- Unused Pens may be used until the expiration date (EXP) printed on the label if the Pen has been kept in the refrigerator.
- Do not freeze your Pen. Throw away (discard) the Pen if it has been frozen.

Used Pens:

- You may store your used Pen at room temperature up to 86°F (30°C) after your injection.
- Keep away from heat and light.
- Keep your Pen and needles out of the sight and reach of children.
- Throw away the Pen 30 days after first use even though the Pen has medicine left in it.
- Throw away the Pen after receiving 4 weekly doses. Attempting to inject any leftover medicine could result in an incomplete dose even though the Pen still has medicine left in it.

Disposing of MOUNJARO KwikPen and pen needles

- Put your used pen needles in an FDA-cleared sharps disposal container right away after use.
- Do not throw away (discard) loose pen needles in your household trash.
- Discard the used Pen in your household trash or FDA-cleared sharps disposal container after you have removed the needle.
- If you do not have an FDA-cleared sharps disposal container, you may use a household container that is:
  - made of a heavy-duty plastic,
  - can be closed with a tight-fitting, puncture-resistant lid, without sharps being able to come out,
  - upright and stable during use,
  - leak-resistant, and
  - properly labeled to warn of hazardous waste inside the container.
- When your sharps disposal container is almost full, you will need to follow your community guidelines for the right way to dispose of your sharps disposal container. There may be state or local laws about how you should throw away (discard) used needles. For more information about safe sharps disposal, and for specific information about sharps disposal in the state you live in, go to the FDA's website at: http://www.fda.gov/safesharpsdisposal.
- Do not dispose of your used sharps disposal container in your household trash unless your community guidelines permit this. Do not recycle your used sharps disposal container.

Troubleshooting

- If you cannot remove the Pen cap, gently twist the Pen cap back and forth, and then pull the Pen cap straight off.
- If the dose knob is hard to push:
  - pushing the dose knob more slowly will make it easier to inject.
  - your needle may be blocked. Put on a new pen needle and prime the Pen.
  - you may have dust, food, or liquid inside the Pen. Throw the Pen away and get a new Pen.
- If the Pen prevents you from turning the dose knob until the is in the dose window:
  - Throw away (discard) the Pen, including the unused medicine. There may not be enough medicine left in the pen to give a full dose. Do not attempt to inject the leftover medicine.

Additional Information:

If you have any questions or problems with MOUNJARO KwikPen:

- Call your healthcare provider
- Call 1-800-Lilly-Rx (1-800-545-5979)
- Visit www.mounjaro.com

Scan this code to launch
www.mounjaro.com

MOUNJARO® and KwikPen® are registered trademarks of Eli Lilly and Company.

Marketed by:
Lilly USA, LLC
Indianapolis, IN 46285, USA

Copyright ©2026, Eli Lilly and Company. All rights reserved.

MOUNJARO KwikPen meets the current dose accuracy and functional requirements of ISO 11608-1.

This Instructions for Use has been approved by the U.S. Food and Drug Administration.

Revised: January 2026

MOUKP-0002-IFU-20260121

Medication Calendar

Use MOUNJARO 1 time a week. Write the day of the week you choose to inject. Inject on this day each week (Example: Monday). |  | I inject my weekly dose on the dates below.
Use MOUNJARO 1 time a week. Write the day of the week you choose to inject. Inject on this day each week (Example: Monday). |  | (Month/Day) | (Month/Day) | (Month/Day) | (Month/Day)

PACKAGE LABEL - Mounjaro Prefilled Pen (Autoinjector) - 2.5 mg/0.5 mL Dose

NDC 0002-1506-80

Mounjaro®

(tirzepatide) injection

2.5 mg/0.5 mL

Use one pen every week.

4 Single-dose prefilled pens

4 x 2.5 mg/0.5 mL prefilled pens

Rx Only

For Subcutaneous Use

Dispense enclosed Medication Guide to each patient.

Lilly

PACKAGE LABEL - Mounjaro Prefilled Pen (Autoinjector) - 5 mg/0.5 mL Dose

NDC 0002-1495-80

Mounjaro®

(tirzepatide) injection

5 mg/0.5 mL

Use one pen every week.

4 Single-dose prefilled pens

4 x 5 mg/0.5 mL prefilled pens

Rx Only

For Subcutaneous Use

Dispense enclosed Medication Guide to each patient.

Lilly

PACKAGE LABEL - Mounjaro Prefilled Pen (Autoinjector) - 7.5 mg/0.5 mL Dose

NDC 0002-1484-80

Mounjaro®

(tirzepatide) injection

7.5 mg/0.5 mL

Use one pen every week.

4 Single-dose prefilled pens

4 x 7.5 mg/0.5 mL prefilled pens

Rx Only

For Subcutaneous Use

Dispense enclosed Medication Guide to each patient.

Lilly

PACKAGE LABEL - Mounjaro Prefilled Pen (Autoinjector) - 10 mg/0.5 mL Dose

NDC 0002-1471-80

Mounjaro®

(tirzepatide) injection

10 mg/0.5 mL

Use one pen every week.

4 Single-dose prefilled pens

4 x 10 mg/0.5 mL prefilled pens

Rx Only

For Subcutaneous Use

Dispense enclosed Medication Guide to each patient.

Lilly

PACKAGE LABEL - Mounjaro Prefilled Pen (Autoinjector) - 12.5 mg/0.5 mL Dose

NDC 0002-1460-80

Mounjaro®

(tirzepatide) injection

12.5 mg/0.5 mL

Use one pen every week.

4 Single-dose prefilled pens

4 x 12.5 mg/0.5 mL prefilled pens

Rx Only

For Subcutaneous Use

Dispense enclosed Medication Guide to each patient.

Lilly

PACKAGE LABEL - Mounjaro Prefilled Pen (Autoinjector) - 15 mg/0.5 mL Dose

NDC 0002-1457-80

Mounjaro®

(tirzepatide) injection

15 mg/0.5 mL

Use one pen every week.

4 Single-dose prefilled pens

4 x 15 mg/0.5 mL prefilled pens

Rx Only

For Subcutaneous Use

Dispense enclosed Medication Guide to each patient.

Lilly

PACKAGE LABEL - Mounjaro Single-Dose Vial - 2.5 mg/0.5 mL Dose

NDC 0002-1152-01

Mounjaro®

(tirzepatide) injection

2.5 mg/0.5 mL

Single-dose Vial - discard unused portion

Rx Only

For Subcutaneous Use

Needles and Syringes are not included

Dispense enclosed Medication Guide to each patient.

Lilly

PACKAGE LABEL - Mounjaro Single-Dose Vial - 5 mg/0.5 mL Dose

NDC 0002-1243-01

Mounjaro®

(tirzepatide) injection

5 mg/0.5 mL

Single-dose Vial - discard unused portion

Rx Only

For Subcutaneous Use

Needles and Syringes are not included

Dispense enclosed Medication Guide to each patient.

Lilly

PACKAGE LABEL - Mounjaro Single-Dose Vial - 7.5 mg/0.5 mL Dose

NDC 0002-2214-01

Mounjaro®

(tirzepatide) injection

7.5 mg/0.5 mL

Single-dose Vial - discard unused portion

Rx Only

For Subcutaneous Use

Needles and Syringes are not included

Dispense enclosed Medication Guide to each patient.

Lilly

PACKAGE LABEL - Mounjaro Single-Dose Vial - 10 mg/0.5 mL Dose

NDC 0002-2340-01

Mounjaro®

(tirzepatide) injection

10 mg/0.5 mL

Single-dose Vial - discard unused portion

Rx Only

For Subcutaneous Use

Needles and Syringes are not included

Dispense enclosed Medication Guide to each patient.

Lilly

PACKAGE LABEL - Mounjaro Single-Dose Vial - 12.5 mg/0.5 mL Dose

NDC 0002-2423-01

Mounjaro®

(tirzepatide) injection

12.5 mg/0.5 mL

Single-dose Vial - discard unused portion

Rx Only

For Subcutaneous Use

Needles and Syringes are not included

Dispense enclosed Medication Guide to each patient.

Lilly

PACKAGE LABEL - Mounjaro Single-Dose Vial - 15 mg/0.5 mL Dose

NDC 0002-3002-01

Mounjaro®

(tirzepatide) injection

15 mg/0.5 mL

Single-dose Vial - discard unused portion

Rx Only

For Subcutaneous Use

Needles and Syringes are not included

Dispense enclosed Medication Guide to each patient.

Lilly

PACKAGE LABEL - Mounjaro Multi-Dose Vial - 2.5 mg/0.6 mL Dose (10 mg/2.4 mL [4.17 mg/mL])

Rx Only

NDC 0002-4052-11

Mounjaro

(tirzepatide) injection

10 mg/2.4 mL
(4.17 mg/mL)

ATTENTION:
Contains 4 doses of 2.5 mg/0.6 mL
2.4 mL MULTI-DOSE VIAL

For Subcutaneous Use

Needles and Syringes are not included

Dispense enclosed Medication Guide to each patient.

Lilly

PACKAGE LABEL - Mounjaro Multi-Dose Vial - 5 mg/0.6 mL Dose (20 mg/2.4 mL [8.33 mg/mL])

Rx Only

NDC 0002-4103-11

Mounjaro

(tirzepatide) injection

20 mg/2.4 mL
(8.33 mg/mL)

ATTENTION:
Contains 4 doses of 5 mg/0.6 mL
2.4 mL MULTI-DOSE VIAL

For Subcutaneous Use

Needles and Syringes are not included

Dispense enclosed Medication Guide to each patient.

Lilly

PACKAGE LABEL - Mounjaro Multi-Dose Vial - 7.5 mg/0.6 mL Dose (30 mg/2.4 mL [12.5 mg/mL])

Rx Only

NDC 0002-4210-11

Mounjaro

(tirzepatide) injection

30 mg/2.4 mL
(12.5 mg/mL)

ATTENTION:
Contains 4 doses of 7.5 mg/0.6 mL
2.4 mL MULTI-DOSE VIAL

For Subcutaneous Use

Needles and Syringes are not included

Dispense enclosed Medication Guide to each patient.

Lilly

PACKAGE LABEL - Mounjaro Multi-Dose Vial - 10 mg/0.6 mL Dose (40 mg/2.4 mL [16.7 mg/mL])

Rx Only

NDC 0002-4304-11

Mounjaro

(tirzepatide) injection

40 mg/2.4 mL
(16.7 mg/mL)

ATTENTION:
Contains 4 doses of 10 mg/0.6 mL
2.4 mL MULTI-DOSE VIAL

For Subcutaneous Use

Needles and Syringes are not included

Dispense enclosed Medication Guide to each patient.

Lilly

PACKAGE LABEL - Mounjaro Multi-Dose Vial - 12.5 mg/0.6 mL Dose (50 mg/2.4 mL [20.8 mg/mL])

Rx Only

NDC 0002-4523-11

Mounjaro

(tirzepatide) injection

50 mg/2.4 mL
(20.8 mg/mL)

ATTENTION:
Contains 4 doses of 12.5 mg/0.6 mL
2.4 mL MULTI-DOSE VIAL

For Subcutaneous Use

Needles and Syringes are not included

Dispense enclosed Medication Guide to each patient.

Lilly

PACKAGE LABEL - Mounjaro Multi-Dose Vial - 15 mg/0.6 mL Dose (60 mg/2.4 mL[25 mg/mL])

Rx Only

NDC 0002-4612-11

Mounjaro

(tirzepatide) injection

60 mg/2.4 mL
(25 mg/mL)

ATTENTION:
Contains 4 doses of 15 mg/0.6 mL
2.4 mL MULTI-DOSE VIAL

For Subcutaneous Use

Needles and Syringes are not included

Dispense enclosed Medication Guide to each patient.

Lilly

PACKAGE LABEL

PACKAGE LABEL – MOUNJARO KwikPen – 2.5 mg per dose (10 mg/2.4 mL [4.17 mg/mL])

NDC 0002-3466-11

Rx Only

Mounjaro®

KwikPen®

(tirzepatide) injection

2.5 mg per dose

10 mg/2.4 mL (4.17 mg/mL)

1 Pen with 4 doses of 2.5 mg

TURN THE DOSE KNOB ALL THE WAY UNTIL YOU SEE A . THIS IS ONE DOSE.

For Single-Patient-Use Only

For Subcutaneous Use

Needles not included

Dispense enclosed Medication Guide to each patient.

Use MOUNJARO KwikPen once weekly

Read the INSTRUCTIONS FOR USE. This product may have different steps than other products.

PACKAGE LABEL

PACKAGE LABEL – MOUNJARO KwikPen – 5 mg per dose (20 mg/2.4 mL [8.33 mg/mL])

NDC 0002-3455-11

Rx Only

Mounjaro®

KwikPen®

(tirzepatide) injection

5 mg per dose

20 mg/2.4 mL (8.33 mg/mL)

1 Pen with 4 doses of 5 mg

TURN THE DOSE KNOB ALL THE WAY UNTIL YOU SEE A . THIS IS ONE DOSE.

For Single-Patient-Use Only

For Subcutaneous Use

Needles not included

Dispense enclosed Medication Guide to each patient.

Use MOUNJARO KwikPen once weekly

Read the INSTRUCTIONS FOR USE. This product may have different steps than other products.

PACKAGE LABEL

PACKAGE LABEL – MOUNJARO KwikPen – 7.5 mg per dose (30 mg/2.4 mL [12.5 mg/mL])

NDC 0002-3444-11

Rx Only

Mounjaro®

KwikPen®

(tirzepatide) injection

7.5 mg per dose

30 mg/2.4 mL (12.5 mg/mL)

1 Pen with 4 doses of 7.5 mg

TURN THE DOSE KNOB ALL THE WAY UNTIL YOU SEE A . THIS IS ONE DOSE.

For Single-Patient-Use Only

For Subcutaneous Use

Needles not included

Dispense enclosed Medication Guide to each patient.

Use MOUNJARO KwikPen once weekly

Read the INSTRUCTIONS FOR USE. This product may have different steps than other products.

PACKAGE LABEL

PACKAGE LABEL – MOUNJARO KwikPen – 10 mg per dose (40 mg/2.4 mL [16.7 mg/mL])

NDC 0002-3433-11

Rx Only

Mounjaro®

KwikPen®

(tirzepatide) injection

10 mg per dose

40 mg/2.4 mL (16.7 mg/mL)

1 Pen with 4 doses of 10 mg

TURN THE DOSE KNOB ALL THE WAY UNTIL YOU SEE A . THIS IS ONE DOSE.

For Single-Patient-Use Only

For Subcutaneous Use

Needles not included

Dispense enclosed Medication Guide to each patient.

Use MOUNJARO KwikPen once weekly

Read the INSTRUCTIONS FOR USE. This product may have different steps than other products.

PACKAGE LABEL

PACKAGE LABEL – MOUNJARO KwikPen – 12.5 mg per dose (50 mg/2.4 mL [20.8 mg/mL])

NDC 0002-3422-11

Rx Only

Mounjaro®

KwikPen®

(tirzepatide) injection

12.5 mg per dose

50 mg/2.4 mL (20.8 mg/mL)

1 Pen with 4 doses of 12.5 mg

TURN THE DOSE KNOB ALL THE WAY UNTIL YOU SEE A . THIS IS ONE DOSE.

For Single-Patient-Use Only

For Subcutaneous Use

Needles not included

Dispense enclosed Medication Guide to each patient.

Use MOUNJARO KwikPen once weekly

Read the INSTRUCTIONS FOR USE. This product may have different steps than other products.

PACKAGE LABEL

PACKAGE LABEL – MOUNJARO KwikPen – 15 mg per dose (60 mg/2.4 mL [25 mg/mL])

NDC 0002-3411-11

Rx Only

Mounjaro®

KwikPen®

(tirzepatide) injection

15 mg per dose

60 mg/2.4 mL (25 mg/mL)

1 Pen with 4 doses of 15 mg

TURN THE DOSE KNOB ALL THE WAY UNTIL YOU SEE A . THIS IS ONE DOSE.

For Single-Patient-Use Only

For Subcutaneous Use

Needles not included

Dispense enclosed Medication Guide to each patient.

Use MOUNJARO KwikPen once weekly

Read the INSTRUCTIONS FOR USE. This product may have different steps than other products.